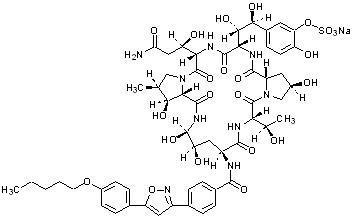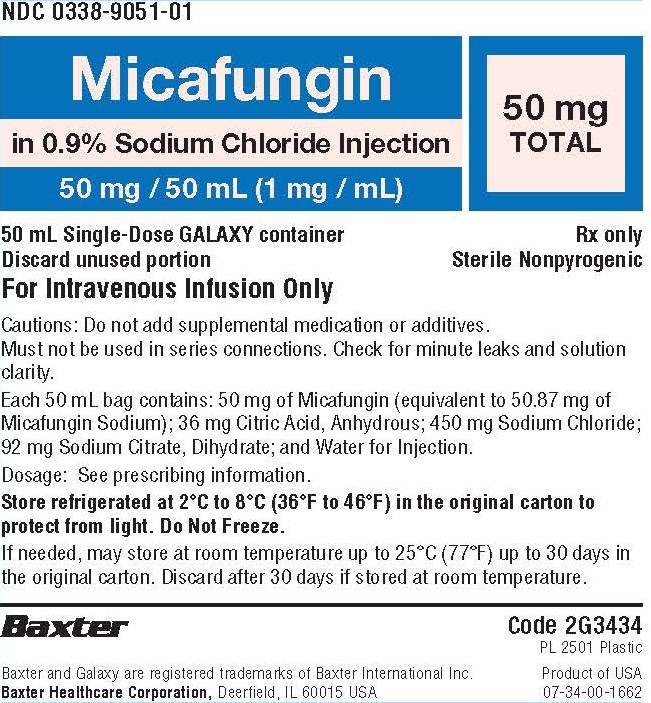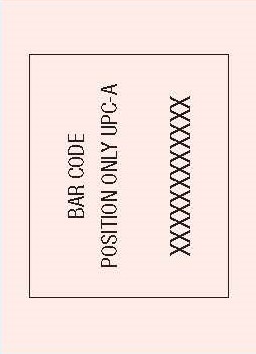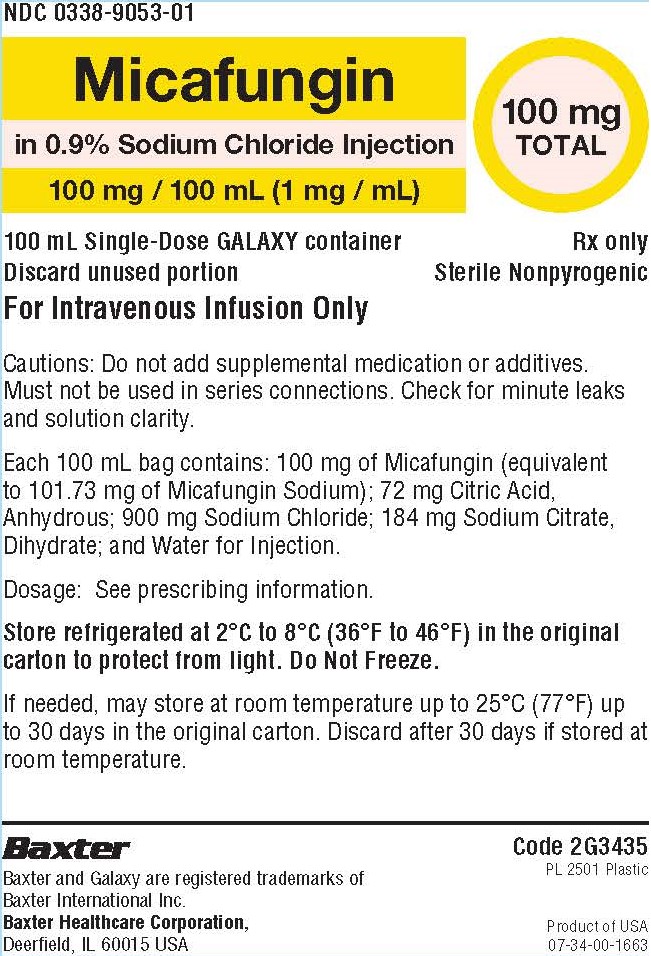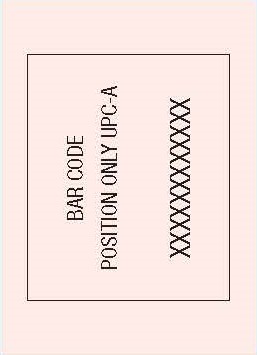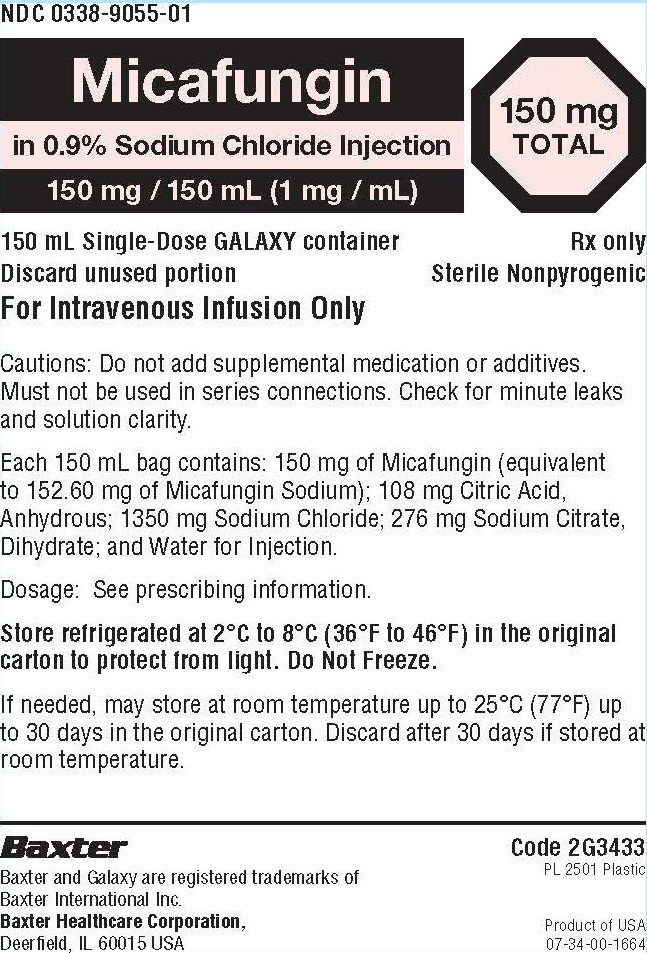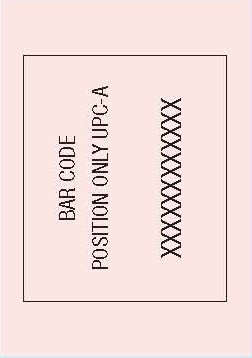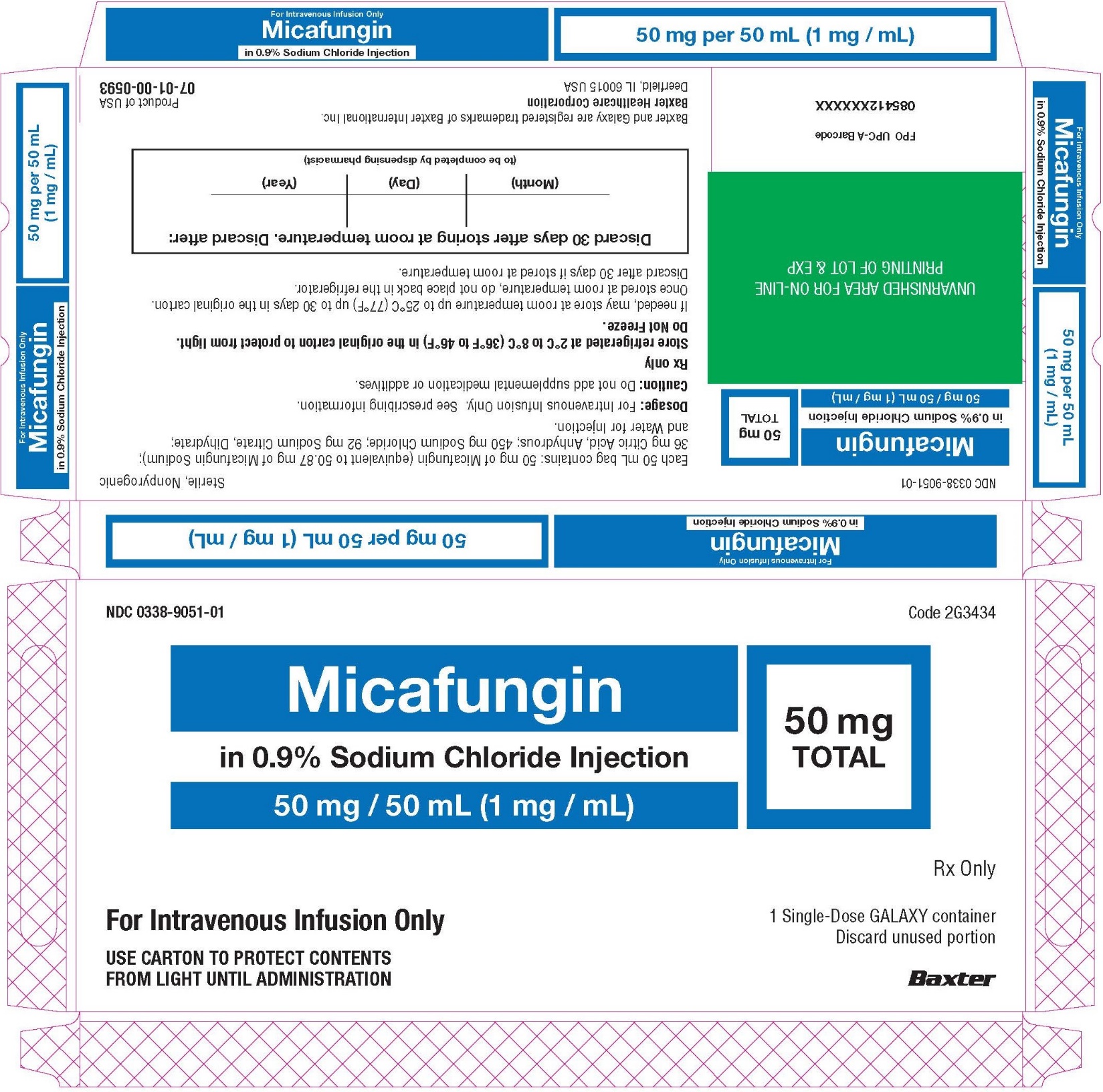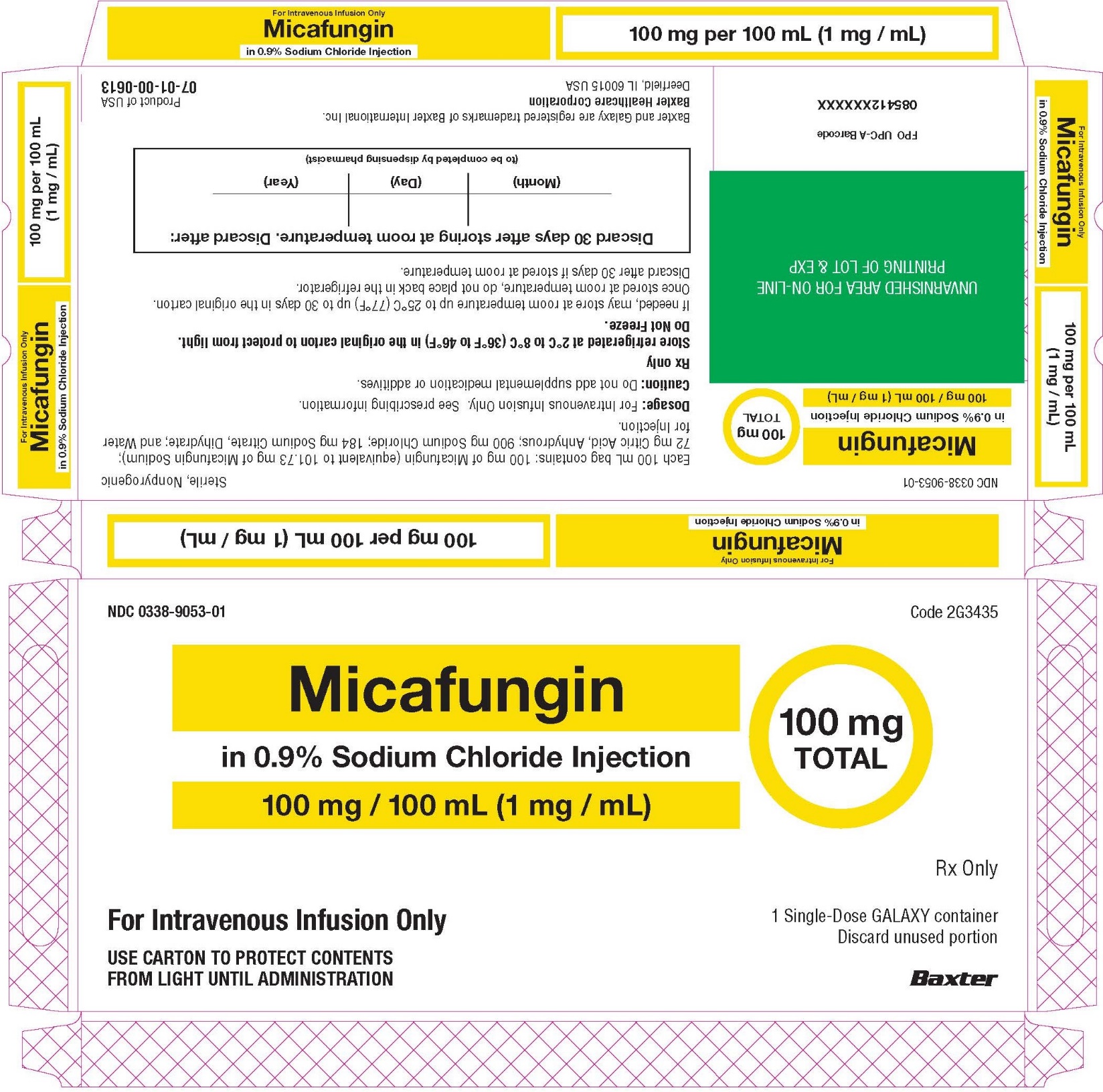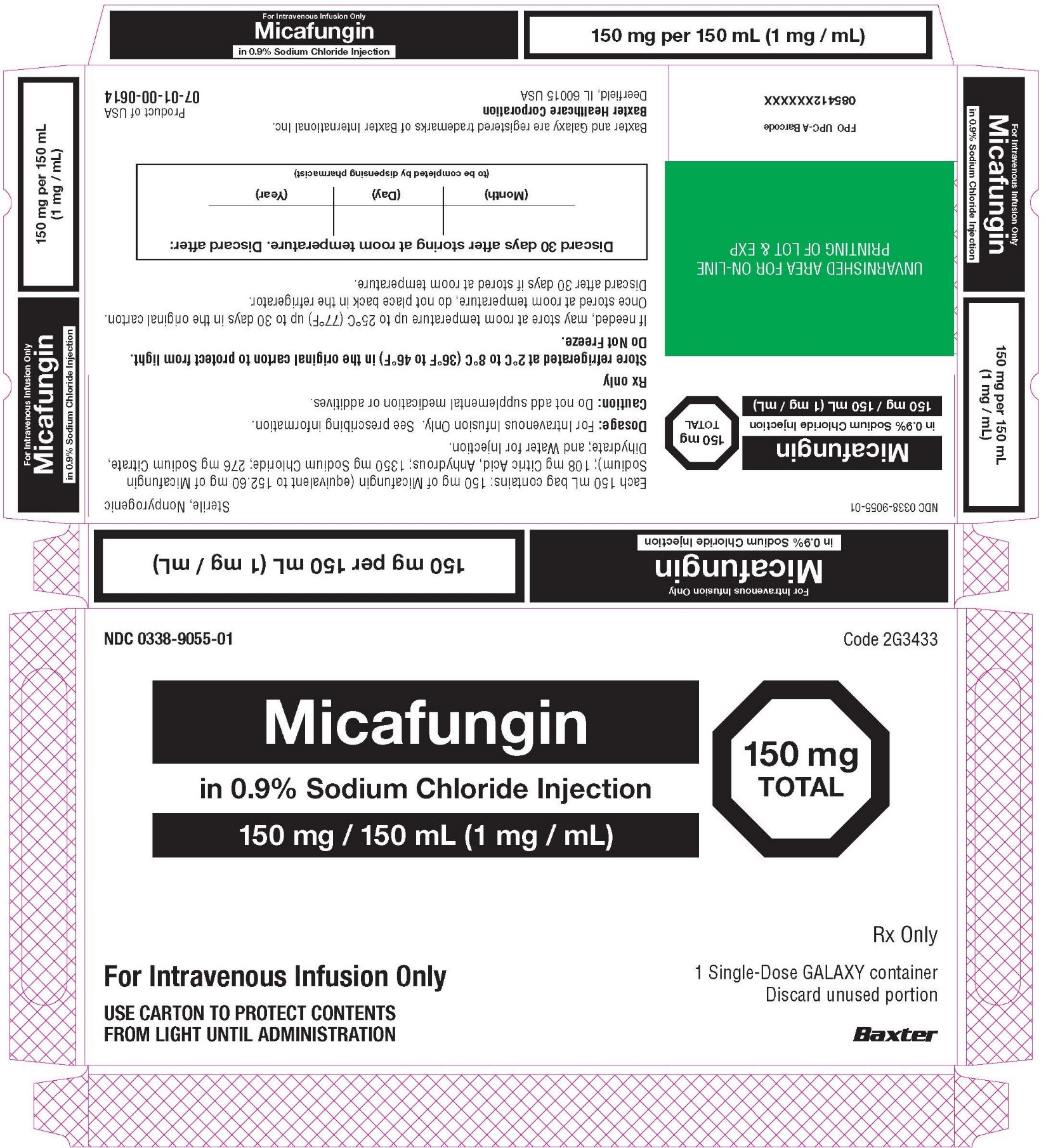 DRUG LABEL: Micafungin in Sodium Chloride
NDC: 0338-9051 | Form: INJECTION
Manufacturer: Baxter Healthcare Corporation
Category: prescription | Type: HUMAN PRESCRIPTION DRUG LABEL
Date: 20230929

ACTIVE INGREDIENTS: MICAFUNGIN SODIUM 50 mg/50 mL
INACTIVE INGREDIENTS: ANHYDROUS CITRIC ACID 36 mg/50 mL; SODIUM CHLORIDE 450 mg/50 mL; TRISODIUM CITRATE DIHYDRATE 92 mg/50 mL; WATER

HIGHLIGHTS OF PRESCRIBING INFORMATION

These highlights do not include all the information needed to use MICAFUNGIN IN SODIUM CHLORIDE INJECTION safely and effectively. See full prescribing information for MICAFUNGIN IN SODIUM CHLORIDE INJECTION.
MICAFUNGIN IN SODIUM CHLORIDE injection, for intravenous use
Initial U.S. Approval: 2005

1 INDICATIONS AND USAGE

Micafungin in Sodium Chloride Injection is an echinocandin indicated in adult and pediatric patients for (1):

- Treatment of Candidemia, Acute Disseminated Candidiasis, Candida Peritonitis and Abscesses in adult and pediatric patients 4 months of age and older for whom appropriate dosing with this formulation can be achieved.
- Treatment of Candidemia, Acute Disseminated Candidiasis, Candida Peritonitis and Abscesses without meningoencephalitis and/or ocular dissemination in pediatric patients younger than 4 months of age for whom appropriate dosing with this formulation can be achieved.
- Treatment of Esophageal Candidiasis in adult and pediatric patients 4 months of age and older for whom appropriate dosing with this formulation can be achieved.
- Prophylaxis of Candida Infections in adult and pediatric patients 4 months of age and older undergoing Hematopoietic Stem Cell Transplantation (HSCT) for whom appropriate dosing with this formulation can be achieved.

Limitations of Use

- The safety and effectiveness of Micafungin in Sodium Chloride Injection have not been established for the treatment of candidemia with meningoencephalitis and/or ocular dissemination in pediatric patients younger than 4 months of age as a higher dose may be needed. (1, 2.4, 8.4)
- Micafungin in Sodium Chloride Injection has not been adequately studied in patients with endocarditis, osteomyelitis or meningoencephalitis due to Candida. (1)
- The efficacy of Micafungin in Sodium Chloride Injection against infections caused by fungi other than Candida has not been established. (1)

2 DOSAGE AND ADMINISTRATION

- If a dose of Micafungin in Sodium Chloride Injection is required that does not equal 50 mg, 100 mg, or 150 mg, this product is not recommended for use and an alternative formulation of micafungin should be considered.

Recommended Dosage Administered by Indication, Weight and Age (2.1, 2.2, 2.3, 2.4, 8.4)

Adult | Pediatric Patients 4 Months and Older 30 kg or less | Pediatric Patients 4 Months and Older greater than 30 kg | Pediatric Patients Younger than 4 Months of Age
Treatment of Candidemia, Acute Disseminated Candidiasis, Candida Peritonitis and Abscesses
100 mg daily | 2 mg/kg/day (maximum 100 mg daily) |  | See below
Treatment of Candidemia, Acute Disseminated Candidiasis, Candida Peritonitis and Abscesses without Meningoencephalitis and/or Ocular Dissemination
See above | See above |  | 4 mg/kg/day
Treatment of Esophageal Candidiasis
150 mg daily | 3 mg/kg/day | 2.5 mg/kg/day (maximum 150 mg daily) | Not approved
Prophylaxis of Candida Infections in HSCT Recipients
50 mg daily | 1 mg/kg/day (maximum 50 mg daily) |  | Not approved

- Infuse over 1 hour. (2.6)
- See Full Prescribing Information for intravenous (IV) directions for preparation for administration instructions. (2.5, 2.6)

3 DOSAGE FORMS AND STRENGTHS

Micafungin in Sodium Chloride Injection: 50 mg/50 mL (1 mg/mL), 100 mg/100 mL (1 mg/mL), and 150 mg/150 mL (1 mg/mL) in single-dose Galaxy containers. (3)

4 CONTRAINDICATIONS

Micafungin in Sodium Chloride Injection is contraindicated in persons with known hypersensitivity to micafungin sodium, any component of Micafungin in Sodium Chloride Injection, or other echinocandins. (4)

5 WARNINGS AND PRECAUTIONS

- Hypersensitivity Reactions: Anaphylaxis and anaphylactoid reactions (including shock) have been observed. Discontinue Micafungin in Sodium Chloride Injection and administer appropriate treatment. (5.1)
- Hematological Effects: Isolated cases of acute intravascular hemolysis, hemolytic anemia and hemoglobinuria have been reported. Monitor rate of hemolysis. Discontinue if severe. (5.2)
- Hepatic Effects: Abnormalities in liver tests; isolated cases of hepatic impairment, hepatitis, and hepatic failure have been observed. Monitor hepatic function. Discontinue if severe dysfunction occurs. (5.3)
- Renal Effects: Elevations in BUN and creatinine; isolated cases of renal impairment or acute renal failure have been reported. Monitor renal function. (5.4)
- Infusion and Injection Site Reactions can occur including rash, pruritus, facial swelling, and vasodilatation. Monitor infusion closely, slow infusion rate if necessary. (2.5, 5.5)
- High Sodium Load: Each 50, 100, and 150 mL Galaxy container contains 200, 400, and 600 mg of sodium, respectively. Avoid use in patients with congestive heart failure, elderly patients, and patients requiring restricted sodium intake. (5.6, 8.5)

6 ADVERSE REACTIONS

- Most common adverse reactions across adult and pediatric clinical trials for all indications include diarrhea, nausea, vomiting, abdominal pain, pyrexia, thrombocytopenia, neutropenia, and headache. (6.1)
- In pediatric patients younger than 4 months of age, the following additional common adverse reactions were reported at an incidence rate of ≥15%: hypokalemia, acidosis, sepsis, anemia, and oxygen saturation decreased. (6.1)

To report SUSPECTED ADVERSE REACTIONS, contact Baxter Healthcare Corporation at 1-866-888-2472 or FDA at 1-800-FDA-1088 or www.fda.gov/medwatch.

7 DRUG INTERACTIONS

Monitor for sirolimus, itraconazole or nifedipine toxicity, and dosage of sirolimus, itraconazole or nifedipine should be reduced, if necessary. (7)

8 USE IN SPECIFIC POPULATIONS

Pregnancy: Based on animal data, Micafungin in Sodium Chloride Injection may cause fetal harm. Advise pregnant women of the risk to the fetus. (8.1)

FULL PRESCRIBING INFORMATION

1 INDICATIONS AND USAGE

Micafungin in Sodium Chloride Injection is indicated for:

- Treatment of Candidemia, Acute Disseminated Candidiasis, Candida Peritonitis and Abscesses in adult and pediatric patients 4 months of age and older for whom appropriate dosing with this formulation can be achieved [see Clinical Studies (14.1) and Use in Specific Populations (8.4)].
- Treatment of Candidemia, Acute Disseminated Candidiasis, Candida Peritonitis and Abscesses without meningoencephalitis and/or ocular dissemination in pediatric patients younger than 4 months of age for whom appropriate dosing with this formulation can be achieved [see Use in Specific Populations (8.4)].
- Treatment of Esophageal Candidiasis in adult and pediatric patients 4 months of age and older for whom appropriate dosing with this formulation can be achieved [see Clinical Studies (14.2)].
- Prophylaxis of Candida Infections in adult and pediatric patients 4 months of age and older undergoing hematopoietic stem cell transplantation for whom appropriate dosing with this formulation can be achieved [see Clinical Studies (14.3)].

Limitations of Use

- The safety and effectiveness of Micafungin in Sodium Chloride Injection have not been established for the treatment of candidemia with meningoencephalitis and/or ocular dissemination in pediatric patients younger than 4 months of age as a higher dose may be needed [see Use in Specific Populations (8.4)].
- Micafungin in Sodium Chloride Injection has not been adequately studied in patients with endocarditis, osteomyelitis and meningoencephalitis due to Candida.
- The efficacy of Micafungin in Sodium Chloride Injection against infections caused by fungi other than Candida has not been established.

2 DOSAGE AND ADMINISTRATION

2.1 Important Administration Instructions

If a dose of Micafungin in Sodium Chloride Injection is required that does not equal 50 mg, 100 mg, or 150 mg, this product is not recommended for use and an alternative formulation of micafungin should be considered.

2.2 Recommended Dosage for Adults

The recommended dosage for adult patients based on indications are shown in Table 1.

Table 1. Micafungin in Sodium Chloride Injection Dosage in Adult Patients
Indication | Recommended Dose Once Daily
Treatment of Candidemia, Acute Disseminated Candidiasis, Candida Peritonitis and Abscesses [In patients treated successfully for candidemia and other Candida infections, the mean duration of treatment was 15 days (range 10 to 47 days).] | 100 mg
Treatment of Esophageal Candidiasis [In patients treated successfully for esophageal candidiasis, the mean duration of treatment was 15 days (range 10 to 30 days).] | 150 mg
Prophylaxis of Candida Infections in HSCT Recipients [In hematopoietic stem cell transplant (HSCT) recipients who experienced success of prophylactic therapy, the mean duration of prophylaxis was 19 days (range 6 to 51 days).] | 50 mg

2.3 Recommended Dosage for Pediatric Patients 4 Months and Older

The recommended dosage for pediatric patients 4 months of age and older based on indication and weight are shown in Table 2.

Table 2. Micafungin in Sodium Chloride Injection Dosage in Pediatric Patients (4 Months of Age and Older) [If a dose of Micafungin in Sodium Chloride Injection is required that does not equal 50 mg, 100 mg, or 150 mg, this product is not recommended for use and an alternative formulation of micafungin should be considered [see Use in Specific Populations (8.4)].]
Indication | Dosage for Pediatric Patients 4 Months of Age and Older
Indication | 30 kg or less | Greater than 30 kg
Treatment of Candidemia, Acute Disseminated Candidiasis, Candida Peritonitis and Abscesses | 2 mg/kg once daily (maximum daily dose 100 mg)
Treatment of Esophageal Candidiasis | 3 mg/kg once daily | 2.5 mg/kg once daily (maximum daily dose 150 mg)
Prophylaxis of Candida Infections in HSCT Recipients | 1 mg/kg once daily (maximum daily dose 50 mg)

2.4 Recommended Dosage for Pediatric Patients Younger than 4 Months of Age

Treatment of Candidemia, Acute Disseminated Candidiasis, Candida Peritonitis and Abscesses without meningoencephalitis and/or ocular dissemination

The recommended dosage is 4 mg/kg once daily. If a dose of Micafungin in Sodium Chloride Injection is required that does not equal 50 mg, 100 mg, or 150 mg, this product is not recommended for use and an alternative formulation of micafungin should be considered.

The safety and effectiveness of Micafungin in Sodium Chloride Injection have not been established for the treatment of candidemia with meningoencephalitis and/or ocular dissemination in pediatric patients younger than 4 months of age as a higher dose may be needed [see Use in Specific Populations (8.4), Clinical Pharmacology (12.3) and Microbiology (12.4)].

2.5 Directions for Administration Preparation and Storage Conditions for Stability

Do not mix or co-infuse Micafungin in Sodium Chloride Injection with other medications. Micafungin has been shown to precipitate when mixed directly with a number of other commonly used medications. Please read this entire section carefully before beginning to prepare for administration.

Preparation for Administration

- No further dilution is necessary.
- Suspend container from support.
- Remove protector from outlet port at bottom of container.
- Attach Intravenous administration set to outlet port. Refer to the manufacturer’s instructions accompanying the administration set for complete directions.
- Check for minute leaks by squeezing container firmly. If leaks are detected, discard solution as sterility may be impaired.
- Parenteral drug products should be inspected visually for particulate matter and discoloration prior to administration, whenever solution and container permit. Do not use if there is any evidence of precipitation or foreign matter. Micafungin in Sodium Chloride Injection is a clear and colorless solution.
- Micafungin in Sodium Chloride Injection is preservative-free. Discard partially used bags. Do not freeze.

Storage Conditions or Stability

- Solution is stable for up to 30 days in the original carton at room temperature up to 25°C (77°F). Once stored at room temperature, do not place back in the refrigerator. Discard Micafungin in Sodium Chloride Injection after 30 days if stored at room temperature [see How Supplied/Storage and Handling (16)].
- Do not Freeze.
- Micafungin in Sodium Chloride Injection does not require light protection during administration.

2.6 Administration Instructions

Adult Patients

Administer Micafungin in Sodium Chloride Injection by intravenous infusion only. Infuse over one hour. More rapid infusions may result in more frequent histamine-mediated reactions [see Warnings and Precautions (5.5)].

Flush an existing intravenous line with Sodium Chloride Injection prior to infusion of Micafungin in Sodium Chloride Injection.

Pediatric Patients

Infuse Micafungin in Sodium Chloride Injection over one hour [see Dosage and Administration (2.3, 2.4)].

3 DOSAGE FORMS AND STRENGTHS

Injection: Micafungin in Sodium Chloride Injection is available as a clear and colorless, sterile, refrigerated, premixed, iso-osmotic, nonpyrogenic solution in ready to use single-dose Galaxy containers as follows:

- 50 mg/50 mL (1 mg/mL), each 50 mL contains 50 mg of micafungin (present as micafungin sodium)
- 100 mg/100 mL (1 mg/mL), each 100 mL contains 100 mg of micafungin (present as micafungin sodium)
- 150 mg/150 mL (1 mg/mL), each 150 mL contains 150 mg of micafungin (present as micafungin sodium)

4 CONTRAINDICATIONS

Micafungin in Sodium Chloride Injection is contraindicated in persons with known hypersensitivity to micafungin, any component of Micafungin in Sodium Chloride Injection, or other echinocandins.

5 WARNINGS AND PRECAUTIONS

5.1 Hypersensitivity Reactions

Isolated cases of serious hypersensitivity (anaphylaxis and anaphylactoid) reactions (including shock) have been reported in patients receiving micafungin for injection. If these reactions occur, Micafungin in Sodium Chloride Injection infusion should be discontinued and appropriate treatment administered.

5.2 Hematological Effects

Acute intravascular hemolysis and hemoglobinuria was seen in a healthy volunteer during infusion of micafungin for injection (200 mg) and oral prednisolone (20 mg). Cases of significant hemolysis and hemolytic anemia have also been reported in patients treated with micafungin for injection. Patients who develop clinical or laboratory evidence of hemolysis or hemolytic anemia during Micafungin in Sodium Chloride Injection therapy should be monitored closely for evidence of worsening of these conditions and evaluated for the risk/benefit of continuing Micafungin in Sodium Chloride Injection therapy.

5.3 Hepatic Effects

Laboratory abnormalities in liver function tests have been seen in healthy volunteers and patients treated with micafungin. In some patients with serious underlying conditions who were receiving micafungin along with multiple concomitant medications, clinical hepatic abnormalities have occurred, and isolated cases of significant hepatic impairment, hepatitis, and hepatic failure have been reported. Patients who develop abnormal liver function tests during Micafungin in Sodium Chloride Injection therapy should be monitored for evidence of worsening hepatic function and evaluated for the risk/benefit of continuing Micafungin in Sodium Chloride Injection therapy.

5.4 Renal Effects

Elevations in BUN and creatinine, and isolated cases of significant renal impairment or acute renal failure have been reported in patients who received micafungin for injection. In fluconazole-controlled trials, the incidence of drug-related renal adverse reactions was 0.4% for micafungin for injection-treated patients and 0.5% for fluconazole-treated patients. Patients who develop abnormal renal function tests during Micafungin in Sodium Chloride Injection therapy should be monitored for evidence of worsening renal function.

5.5 Infusion and Injection Site Reactions

Possible histamine-mediated symptoms have been reported with micafungin for injection, including rash, pruritus, facial swelling, and vasodilatation. Slow the infusion rate if infusion reaction occurs [see Dosage and Administration (2.6)].

Injection site reactions, including phlebitis and thrombophlebitis have been reported, at micafungin for injection doses of 50 to 150 mg/day. These reactions tended to occur more often in patients receiving micafungin for injection via peripheral intravenous administration [see Adverse Reactions (6.1)].

5.6 High Sodium Load

Each 50 mg/50 mL Galaxy container of Micafungin in Sodium Chloride Injection contains 200 mg of sodium, each 100 mg/100 mL Galaxy container of Micafungin in Sodium Chloride Injection contains 400 mg of sodium, and each 150 mg/150 mL Galaxy container of Micafungin in Sodium Chloride Injection contains 600 mg of sodium. Avoid use of Micafungin in Sodium Chloride Injection in patients with congestive heart failure, elderly patients, and patients requiring restricted sodium intake.

6 ADVERSE REACTIONS

The following clinically significant adverse reactions are described elsewhere in the labeling:

- Hypersensitivity Reactions [see Warnings and Precautions (5.1)]
- Hematological Effects [see Warnings and Precautions (5.2)]
- Hepatic Effects [see Warnings and Precautions (5.3)]
- Renal Effects [see Warnings and Precautions (5.4)]
- Infusion and Injection Site Reactions [see Warnings and Precautions (5.5)]
- High Sodium Load [see Warnings and Precautions (5.6)]

6.1 Clinical Trials Experience

Because clinical trials are conducted under widely varying conditions, adverse reaction rates observed in clinical trials of micafungin for injection cannot be directly compared to rates in clinical trials of another drug and may not reflect the rates observed in practice.

The overall safety of micafungin for injection was assessed in 520 healthy volunteers and 3417 adult and pediatric patients who received single or multiple doses of micafungin for injection across 50 clinical trials, including the invasive candidiasis, esophageal candidiasis and prophylaxis trials. The doses of micafungin for injection administered included doses above and below the recommended doses [see Dosage and Administration (2.1, 2.2, 2.3)] and ranged from 0.75 mg/kg to 15 mg/kg in pediatric patients and 12.5 mg to 150 mg/day or greater in adults.

Clinical Trials Experience in Adults

In clinical trials with micafungin for injection, 2497/2748 (91%) adult patients experienced at least one adverse reaction.

Candidemia and Other Candida Infections

In a randomized, double-blind trial for the treatment of candidemia and other Candida infections, adverse reactions occurred in 183/200 (92%) and 171/193 (89%) patients in the micafungin for injection 100 mg/day, and caspofungin (70 mg loading dose followed by 50 mg/day dose) treatment groups, respectively. Selected adverse reactions occurring in 5% or more of the patients and more frequently in the micafungin for injection treatment group, are shown in Table 3.

Table 3. Selected [During IV Treatment + 3 days.] Adverse Reactions in Adult Patients with Candidemia and Other Candida Infections
Adverse Reactions by System Organ Class [Within a system organ class, patients may experience more than 1 adverse reactions] | Micafungin for Injection 100 mg n (%) | Caspofungin [70 mg loading dose on day 1 followed by 50 mg/day thereafter (caspofungin).] n (%)
Number of Patients | 200 | 193
Gastrointestinal Disorders | 81 (41) | 76 (39)
Diarrhea | 15 (8) | 14 (7)
Vomiting | 18 (9) | 16 (8)
Metabolism and Nutrition Disorders | 77 (39) | 73 (38)
Hypoglycemia | 12 (6) | 9 (5)
Hyperkalemia | 10 (5) | 5 (3)
General Disorders/Administration Site Conditions | 59 (30) | 51 (26)
Investigations | 36 (18) | 37 (19)
Blood Alkaline Phosphatase Increased | 11 (6) | 8 (4)
Cardiac Disorders | 35 (18) | 36 (19)
Atrial Fibrillation | 5 (3) | 0

Patient base: all randomized patients who received at least 1 dose of trial drug.

In a second, supportive, randomized, double-blind trial for the treatment of candidemia and other Candida infections, adverse reactions occurred in 245/264 (93%) and 250/265 (94%) adult and pediatric patients in the micafungin for injection (100 mg/day) and amphotericin B liposome (3 mg/kg/day) treatment groups, respectively. In this trial, the following adverse reactions were reported in patients at least 16 years of age in the micafungin for injection and amphotericin B liposome treatment groups, respectively: nausea (10% vs. 8%), diarrhea (11% vs. 11%), vomiting (13% vs. 9%), abnormal liver tests (4% vs. 3%), increased aspartate aminotransferase (3% vs. 2%), and increased blood alkaline phosphatase (3% vs. 2%).

Esophageal Candidiasis

In a randomized, double-blind study for treatment of esophageal candidiasis, a total of 202/260 (78%) patients who received micafungin for injection 150 mg/day and 186/258 (72%) patients who received intravenous fluconazole 200 mg/day experienced an adverse reaction. Adverse reactions resulting in discontinuation were reported in 17 (7%) micafungin for injection-treated patients; and in 12 (5%) fluconazole-treated patients. Selected treatment-emergent adverse reactions occurring in 5% or more of the patients and more frequently in the micafungin for injection group, are shown in Table 4.

Table 4. Selected [During treatment + 3 days.] Adverse Reactions in Adult Patients with Esophageal Candidiasis
Adverse Reactions by System Organ Class [Within a system organ class, patients may experience more than 1 adverse reaction.] | Micafungin for Injection 150 mg/day n (%) | Fluconazole 200 mg/day n (%)
Number of Patients | 260 | 258
Gastrointestinal Disorders | 84 (32) | 93 (36)
Diarrhea | 27 (10) | 29 (11)
Nausea | 20 (8) | 23 (9)
Vomiting | 17 (7) | 17 (7)
General Disorders/Administration Site Conditions | 52 (20) | 45 (17)
Pyrexia | 34 (13) | 21 (8)
Nervous System Disorders | 42 (16) | 40 (16)
Headache | 22 (9) | 20 (8)
Vascular Disorders | 54 (21) | 21 (8)
Phlebitis | 49 (19) | 13 (5)
Skin and Subcutaneous Tissue Disorders | 36 (14) | 26 (10)
Rash | 14 (5) | 6 (2)

Patient base: all randomized patients who received at least 1 dose of trial drug.

Prophylaxis of Candida Infections in Hematopoietic Stem Cell Transplant Recipients

A double-blind trial was conducted in a total of 882 patients scheduled to undergo an autologous or allogeneic hematopoietic stem cell transplant. The median duration of treatment was 18 days (range 1 to 51 days) in both treatment arms.

All adult patients who received micafungin for injection (382) or fluconazole (409) experienced at least one adverse reaction during the study. Treatment-emergent adverse reactions resulting in micafungin for injection discontinuation were reported in 15 (4%) adult patients; while those resulting in fluconazole discontinuation were reported in 32 (8%). Selected adverse reactions reported in 15% or more of adult patients and more frequently in the micafungin for injection treatment arm, are shown in Table 5.

Table 5. Selected Adverse Reactions in Adult Patients During Prophylaxis of Candida Infection in Hematopoietic Stem Cell Transplant Recipients
System Organ Class | Micafungin for Injection 50 mg/day n (%) | Fluconazole 400 mg/day n (%)
Number of Patients | 382 | 409
Gastrointestinal Disorders | 377 (99) | 404 (99)
Diarrhea | 294 (77) | 327 (80)
Nausea | 270 (71) | 290 (71)
Vomiting | 252 (66) | 274 (67)
Abdominal Pain | 100 (26) | 93 (23)
Blood and Lymphatic System Disorders | 368 (96) | 385 (94)
Neutropenia | 288 (75) | 297 (73)
Thrombocytopenia | 286 (75) | 280 (69)
Skin and Subcutaneous Tissue Disorders | 257 (67) | 275 (67)
Rash | 95 (25) | 91 (22)
Nervous System Disorders | 250 (65) | 254 (62)
Headache | 169 (44) | 154 (38)
Psychiatric Disorders | 233 (61) | 235 (58)
Insomnia | 142 (37) | 140 (34)
Anxiety | 84 (22) | 87 (21)
Cardiac Disorders | 133 (35) | 138 (34)
Tachycardia | 99 (26) | 91 (22)
Patient base: all randomized adult patients who received at least 1 dose of trial drug.

Other selected adverse reactions reported at less than 5% in adult clinical trials are listed below:

- Blood and lymphatic system disorders: coagulopathy, pancytopenia, thrombotic thrombocytopenic purpura
- Cardiac disorders: cardiac arrest, myocardial infarction, pericardial effusion
- General disorders and administration site conditions: infusion reaction, injection site thrombosis
- Hepatobiliary disorders: hepatocellular damage, hepatomegaly, jaundice, hepatic failure
- Immune disorders: hypersensitivity, anaphylactic reaction
- Metabolism and nutrition disorders: hypernatremia, hypokalemia
- Nervous system disorders: convulsions, encephalopathy, intracranial hemorrhage
- Psychiatric disorders: delirium
- Skin and subcutaneous tissue disorders: urticaria

Clinical Trials Experience in Pediatric Patients

The safety of micafungin for injection was assessed in 593 pediatric patients, 425 of whom were 4 months through 16 years of age and 168 of whom were 3 days to less than 4 months of age who received at least one dose of micafungin for injection across 15 clinical trials.

Of the 425 pediatric patients, 4 months through 16 years of age enrolled in 11 clinical trials, 235 (55%) were male, 290 (68%) were white, with the following age distribution: 62 (15%) 4 months to <2 years, 108 (25%) 2 to 5 years, 140 (33%) 6 to 11 years, and 115 (27%) 12 to 16 years of age. The mean treatment duration was 26.1 days. A total of 246 patients received at least one dose of micafungin for injection ranging from 2 to 10 mg/kg. Overall, 388/425 (91%) patients experienced at least one adverse reaction. Adverse reactions occurring in ≥15% or more of micafungin-treated pediatric patients 4 months of age and older are: vomiting (32%), diarrhea (24%), pyrexia (24%), hypokalemia (22%), nausea (21%), mucosal inflammation (19%), thrombocytopenia (19%), abdominal pain (18%), headache (15%), and hypertension (15%).

Two randomized, double-blind active-controlled trials included pediatric patients. In the invasive candidiasis/candidemia trial, the efficacy and safety of micafungin for injection (2 mg/kg/day for patients weighing 40 kg or less and 100 mg/day for patients weighing greater than 40 kg) was compared to amphotericin B liposome (3 mg/kg/day) in 112 pediatric patients. Treatment-emergent adverse reactions occurred in 51/56 (91%) of patients in the micafungin for injection group and 52/56 (93%) of patients in the amphotericin B liposome group. Treatment-emergent adverse reactions resulting in drug discontinuation were reported in 2 (4%) micafungin for injection-treated pediatric patients and in 9 (16%) amphotericin B liposome-treated pediatric patients.

The prophylaxis study in patients undergoing HSCT investigated the efficacy of micafungin for injection (1 mg/kg/day for patients weighing 50 kg or less and 50 mg/day for patients weighing greater than 50 kg) as compared to fluconazole (8 mg/kg/day for patients weighing 50 kg or less and 400 mg/day for patients weighing greater than 50 kg). All 91 pediatric patients experienced at least one treatment-emergent adverse reaction. Three (7%) pediatric patients discontinued micafungin for injection due to adverse reaction, while one (2%) patient discontinued fluconazole.

Selected adverse reactions, occurring in 15% or more of the patients and more frequently in a micafungin for injection group, for the two comparative trials are shown in Table 6.

Table 6. Selected Adverse Reactions in Pediatric Patients with Candidemia and Other Candida Infections (C/IC), and in Hematopoietic Stem-Cell Recipients During Prophylaxis of Candida Infections
Adverse Reactions [Within a system organ class, patients may experience more than 1 adverse reaction.] | C/IC [Study population included 20 pediatric patients younger than 4 months of age (10 in each arm).] |  | Prophylaxis
Adverse Reactions [Within a system organ class, patients may experience more than 1 adverse reaction.] | Micafungin for Injection n = 56 n (%) | Amphotericin B liposome n = 56 n (%) | Micafungin for Injection n = 43 n (%) | Fluconazole n = 48 n (%)
Gastrointestinal disorders | 22 (40) | 18 (32) | 43 (100) | 45 (94)
Vomiting | 10 (18) | 8 (14) | 28 (65) | 32 (67)
Diarrhea | 4 (7) | 5 (9) | 22 (51) | 31 (65)
Nausea | 4 (7) | 4 (7) | 30 (70) | 25 (52)
Abdominal pain | 2 (4) | 2 (4) | 15 (35) | 12 (25)
Abdominal distension | 1 (2) | 1 (2) | 8 (19) | 6 (13)
General disorders and administration site conditions | 14 (25) | 14 (25) | 41 (95) | 46 (96)
Pyrexia | 5 (9) | 9 (16) | 26 (61) | 31 (65)
Infusion-related reaction | 0 | 3 (5) | 7 (16) | 4 (8)
Skin and subcutaneous tissue disorders | 11 (20) | 8 (14) | 33 (77) | 38 (79)
Pruritus | 0 | 1 (2) | 14 (33) | 15 (31)
Rash | 1 (2) | 1 (2) | 13 (30) | 13 (27)
Urticaria | 0 | 1 (2) | 8 (19) | 4 (8)
Respiratory, thoracic and mediastinal disorders | 9 (16) | 13 (23) | 30 (70) | 33 (69)
Epistaxis | 0 | 0 | 4 (9) | 8 (17)
Blood and lymphatic system disorders | 17 (30) | 13 (23) | 40 (93) | 44 (92)
Thrombocytopenia | 5 (9) | 3 (5) | 31 (72) | 37 (77)
Neutropenia | 3 (5) | 4 (7) | 33 (77) | 34 (71)
Anemia | 10 (18) | 6 (11) | 22 (51) | 24 (50)
Febrile neutropenia | 0 | 0 | 7 (16) | 7 (15)
Investigations | 12 (21) | 8 (14) | 24 (56) | 25 (52)
Alanine aminotransferase increased | 0 | 0 | 7 (16) | 1 (2)
Urine output decreased | 0 | 0 | 10 (23) | 8 (17)
Cardiac disorders | 7 (13) | 3 (5) | 10 (23) | 17 (35)
Tachycardia | 2 (4) | 1 (2) | 7 (16) | 12 (25)
Renal and urinary disorders | 4 (7) | 4 (7) | 16 (37) | 15 (31)
Hematuria | 0 | 0 | 10 (23) | 7 (15)
Psychiatric disorders | 3 (5) | 1 (2) | 20 (47) | 9 (19)
Anxiety | 0 | 0 | 10 (23) | 3 (6)

Other clinically significant adverse reactions reported at less than 15% in pediatric clinical trials are listed below:

- Hepatobiliary disorders: hyperbilirubinemia
- Investigations: liver tests abnormal
- Renal Disorders: renal failure

Clinical Trials Experience in Pediatric Patients Younger than 4 Months of Age

The safety of micafungin for injection was assessed in 168 pediatric patients younger than 4 months of age who received varying doses of micafungin for injection in 9 clinical trials. The mean treatment duration was 16.6 days. A total of 59 patients received micafungin for injection at doses ≤4 mg/kg/day and 109 patients received micafungin for injection doses >4 mg/kg/day [5 to 15 mg/kg/day (approximately 1.3 to 3.8 times the recommended dosage in pediatric patients less than 4 months old)].

The adverse reaction profile of micafungin for injection in pediatric patients younger than 4 months of age was generally comparable to that of pediatric patients 4 months of age and older and adults. The most frequent adverse reactions (≥15%) in pediatric patients younger than 4 months old receiving a micafungin for injection dose of approximately 4 mg/kg/day included hypokalemia (25%), thrombocytopenia (25%), acidosis (20%), sepsis (20%), anemia (15%), oxygen saturation decreased (15%), and vomiting (15%). No new safety signals were seen in patients who received 5 to 15 mg/kg/day [see Use in Specific Populations (8.4)].

Additional clinically significant adverse reactions reported in less than 15% of pediatric patients younger than 4 months of age who received approximately 4 mg/kg/day are listed below:

- Blood and Lymphatic System Disorders: leukocytosis, thrombocytosis, coagulation disorder neonatal
- Gastrointestinal Disorders: hematochezia, intestinal perforation, ascites, ileus, intestinal infarction, diarrhea, abdominal distension
- General Disorders and Administration Site Conditions: peripheral swelling, generalized edema, pyrexia, infusion site extravasation, edema neonatal
- Hepatobiliary Disorders: hyperbilirubinemia
- Investigations: blood lactate dehydrogenase increased, blood urea increased, ECG QRS complex prolonged
- Vascular Disorders: neonatal hypotension, thrombophlebitis
- Musculoskeletal and connective tissue disorders: hypertonia neonatal
- Respiratory, thoracic and mediastinal disorders: pleural effusion, respiratory failure, neonatal aspiration, respiratory distress
- Metabolism and nutrition disorders: hyperglycemia, dehydration, hypocalcemia, hypermagnesemia

6.2 Postmarketing Experience

The following adverse reactions have been identified during post-approval use of micafungin for injection. Because these reactions are reported voluntarily from a population of uncertain size, it is not always possible to reliably estimate their frequency or establish a causal relationship to drug exposure.

- Blood and lymphatic system disorders: disseminated intravascular coagulation
- Hepatobiliary disorders: hepatic disorder
- Renal and urinary disorders: renal impairment
- Skin and subcutaneous tissue disorders: Stevens-Johnson syndrome, toxic epidermal necrolysis
- Vascular disorders: shock

7 DRUG INTERACTIONS

7.1 Effect of Other Drugs on Micafungin in Sodium Chloride Injection

CYP3A4, CYP2C9 and CYP2C19 Inhibitors

Co-administration of Micafungin in Sodium Chloride Injection with cyclosporine, itraconazole, voriconazole and fluconazole did not alter the pharmacokinetics of micafungin.

CYP2C19 and CYP3A4 Inducer

Co-administration of Micafungin in Sodium Chloride Injection with rifampin and ritonavir did not alter the pharmacokinetics of micafungin.

Co-administration of Micafungin in Sodium Chloride Injection with Other Drugs

Co-administration of Micafungin in Sodium Chloride Injection with mycophenolate mofetil (MMF), amphotericin B, tacrolimus, prednisolone, sirolimus and nifedipine did not alter the pharmacokinetics of micafungin.

7.2 Effect of Micafungin in Sodium Chloride Injection on Other Drugs

CYP3A4 Substrates

There was no effect of single or multiple doses of micafungin for injection on cyclosporine, tacrolimus, prednisolone, voriconazole and fluconazole pharmacokinetics.

Sirolimus AUC was increased by 21% with no effect on Cmax in the presence of steady-state micafungin for injection compared with sirolimus alone. Nifedipine AUC and Cmax were increased by 18% and 42%, respectively, in the presence of steady-state micafungin for injection compared with nifedipine alone. Itraconazole AUC and Cmax were increased by 22% and 11%, respectively. Patients receiving sirolimus, nifedipine, and itraconazole in combination with micafungin for injection should be monitored for sirolimus, nifedipine, and itraconazole toxicity and the sirolimus, nifedipine, and itraconazole dosage should be reduced if necessary.

UDP-Glycosyltransferase Substrate

Co-administration of mycophenolate mofetil (MMF) with micafungin for injection did not alter the pharmacokinetics of MMF.

8 USE IN SPECIFIC POPULATIONS

8.1 Pregnancy

Risk Summary

Based on findings from animal studies, Micafungin for Injection may cause fetal harm when administered to a pregnant woman (see Data). There is insufficient human data on the use of micafungin for injection in pregnant women to inform a drug-associated risk of adverse developmental outcomes. In animal reproduction studies, intravenous administration of micafungin sodium to pregnant rabbits during organogenesis at doses four times the maximum recommended human dose resulted in visceral abnormalities and increased abortion (see Data). Advise pregnant women of the risk to the fetus.

The estimated background risk of major birth defects and miscarriage for the indicated populations is unknown. All pregnancies have a background risk of birth defect, loss, or other adverse outcomes. In the U.S. general population, the estimated background risk of major birth defects and miscarriage in clinically recognized pregnancies is 2 to 4% and 15 to 20%, respectively.

Data

Animal Data

In an embryo-fetal toxicity study in pregnant rabbits, intravenous administration of micafungin sodium during organogenesis (days 6 to 18 of gestation) resulted in fetal visceral abnormalities and abortion at 32 mg/kg, a dose equivalent to four times the recommended human dose based on body surface area comparisons. Visceral abnormalities included abnormal lobation of the lung, levocardia, retrocaval ureter, anomalous right subclavian artery, and dilatation of the ureter.

8.2 Lactation

Risk Summary

There are no data on the presence of micafungin in human milk, the effects on the breast-fed infant or the effects on milk production. Micafungin was present in the milk of lactating rats following intravenous administration. When a drug is present in animal milk, it is likely that the drug will be present in human milk. The developmental and health benefits of breastfeeding should be considered along with the mother’s clinical need for Micafungin in Sodium Chloride Injection, and any potential adverse effects on the breast-fed child from Micafungin in Sodium Chloride Injection, or from the underlying maternal condition.

8.4 Pediatric Use

Micafungin in Sodium Chloride Injection is indicated in pediatric patients for whom appropriate dosing with this formulation can be achieved. Because of the limitations of the available strengths and administration requirements (i.e., administration of fractional doses is not recommended) of Micafungin in Sodium Chloride Injection, and to avoid unintentional overdose, this product is not recommended for use if a dose of Micafungin in Sodium Chloride Injection that does not equal 50 mg, 100 mg, or 150 mg is required, and an alternative formulation of micafungin should be considered [see Dosage and Administration (2.3, 2.4)].

Pediatric Patients 4 Months of Age and Older

The safety and effectiveness of micafungin for injection for the treatment of esophageal candidiasis, candidemia, acute disseminated candidiasis, Candida peritonitis and abscesses, esophageal candidiasis, and for prophylaxis of Candida infections in patients undergoing HSCT have been established in pediatric patients 4 months of age and older. Use of micafungin for these indications and in this age group is supported by evidence from adequate and well-controlled studies in adult and pediatric patients with additional pharmacokinetic and safety data in pediatric patients 4 months of age and older [see Indications and Usage (1), Adverse Reactions (6.1), Clinical Pharmacology (12.3), and Clinical Studies (14)].

Pediatric Patients Younger than 4 Months of Age

Treatment of Candidemia, Acute Disseminated Candidiasis, Candida Peritonitis and Abscesses Without Meningoencephalitis and/or Ocular Dissemination in Pediatric Patients Younger Than 4 Months of Age

The safety and effectiveness of micafungin for injection for the treatment of candidemia, acute disseminated candidiasis, Candida peritonitis and abscesses without meningoencephalitis and/or ocular dissemination at a dosage of 4 mg/kg once daily have been established in pediatric patients younger than 4 months of age. This use and dosage of micafungin for injection are supported by evidence from adequate and well-controlled studies in adult and pediatric patients 4 months of age and older with additional pharmacokinetic and safety data in pediatric patients younger than 4 months of age [see Adverse Reactions (6.1) and Clinical Pharmacology (12.3)].

Treatment of Candidemia, Acute Disseminated Candidiasis, Candida Peritonitis and Abscesses With Meningoencephalitis and/or Ocular Dissemination in Pediatric Patients Younger Than 4 Months of Age

The safety and effectiveness of micafungin for injection have not been established for the treatment of candidemia with meningoencephalitis and/or ocular dissemination in pediatric patients younger than 4 months of age.

In a rabbit model of hematogenous Candida meningoencephalitis (HCME) with Candida albicans (minimum inhibitory concentration of 0.125 mcg/mL), a decrease in mean fungal burden in central nervous system (CNS) compartments assessed as the average of combined fungal burden in the cerebrum, cerebellum, and spinal cord relative to untreated controls, was observed with increasing micafungin dosages administered once daily for 7 days. Data from the rabbit model suggest that a micafungin dose regimen of 4 mg/kg once daily is inadequate to treat meningoencephalitis and that a dose regimen of approximately 10 to 25 mg/kg once daily may be necessary to lower fungal burden in the CNS in pediatric patients younger than 4 months of age [see Microbiology (12.4)]. In this rabbit model, micafungin concentrations could not be reliably detected in cerebrospinal fluid (CSF). Due to limitations of the study design, the clinical significance of a decreased CNS fungal burden in the rabbit HCME model is uncertain.

A randomized controlled trial evaluated a micafungin for injection dose regimen of 10 mg/kg once daily in pediatric patients younger than 4 months of age with suspected or proven Candida meningoencephalitis. Fungal-free survival at 1 week after end of therapy was observed in 60% of micafungin for injection-treated vs. 70% of amphotericin B-treated patients, and all-cause mortality was 15% vs. 10%, respectively. However, because this study was terminated early and enrolled only 30 pediatric patients younger than 4 months of age (20 treated with micafungin for injection and 10 treated with amphotericin B) which was 13% of the planned enrollment for the study, no conclusions can be drawn regarding efficacy of micafungin for injection at this dose regimen.

In six uncontrolled, open-label studies, and a neonatal intensive care unit (ICU) medical records database, pediatric patients younger than 4 months of age with suspected Candida meningoencephalitis or disseminated candidemia received micafungin for injection at dose regimens ranging from 5 to 15 mg/kg once daily. Across the entire micafungin for injection development program, only 6 pediatric patients with proven Candida meningoencephalitis were treated with dosages of 2 mg/kg, 8 mg/kg and 10 mg/kg once daily. Micafungin was detected in the CSF of pediatric patients with suspected Candida meningoencephalitis. No conclusions regarding the efficacy of a particular dosage of micafungin for injection or the penetration of micafungin into the CSF can be drawn due to limitations of the data, including but not limited to, multiple confounding factors, variable study designs, and limited numbers of patients. No new safety signals were observed with the use of micafungin for injection at dosages of 5 to 15 mg/kg once daily in pediatric patients younger than 4 months of age, and there was no discernible dose-response for adverse events.

Although the dosage for the treatment of candidemia with meningoencephalitis has not been established, antifungal activity in various CNS compartments in the rabbit HCME model and limited clinical trial data suggest that in patients younger than 4 months of age, dose regimens 10 mg/kg once daily or higher may be necessary for the treatment of candidemia with meningoencephalitis. Safety data from clinical studies for micafungin for injection at dose regimens of 10 to 15 mg/kg once daily in pediatric patients younger than 4 months of age did not reveal new safety signals.

Treatment of Esophageal Candidiasis and Prophylaxis of Candida Infections in Patients Undergoing Hematopoietic Stem Cell Transplantation in Pediatric Patients Younger Than 4 Months of Age

The safety and effectiveness of micafungin for injection in pediatric patients younger than 4 months of age have not been established for the:

- Treatment of esophageal candidiasis
- Prophylaxis of Candida infections in patients undergoing hematopoietic stem cell transplantation

8.5 Geriatric Use

A total of 418 subjects in clinical studies of micafungin for injection were 65 years of age and older, and 124 subjects were 75 years of age and older. No overall differences in safety and effectiveness were observed between these subjects and younger subjects. Other reported clinical experience has not identified differences in responses between the elderly and younger patients, but greater sensitivity of some older individuals cannot be ruled out. The exposure and disposition of a 50 mg micafungin for injection dose administered as a single 1-hour infusion to 10 healthy subjects aged 66 to 78 years were not significantly different from those in 10 healthy subjects aged 20 to 24 years. No dose adjustment is necessary for the elderly.

Each 50 mg/50 mL Galaxy container of Micafungin in Sodium Chloride Injection contains 200 mg of sodium, each 100 mg/100 mL Galaxy container of Micafungin in Sodium Chloride Injection contains 400 mg of sodium, and each 150 mg/150 mL Galaxy container of Micafungin in Sodium Chloride Injection contains 600 mg of sodium. The geriatric population may respond with a blunted natriuresis to salt loading. This may be clinically important with regard to such diseases as congestive heart failure and other conditions requiring restricted sodium intake [see Warnings and Precautions (5.6)].

8.6 Use in Patients with Renal Impairment

Micafungin in Sodium Chloride Injection does not require dose adjustment in patients with renal impairment. Supplementary dosing should not be required following hemodialysis [see Clinical Pharmacology (12.3)].

8.7 Use in Patients with Hepatic Impairment

Dose adjustment of Micafungin in Sodium Chloride Injection is not required in patients with mild, moderate, or severe hepatic impairment [see Clinical Pharmacology (12.3)].

8.8 Race and Gender

No dose adjustment of Micafungin in Sodium Chloride Injection is required based on gender or race. After 14 daily doses of 150 mg to healthy subjects, micafungin AUC in women was greater by approximately 23% compared with men, due to smaller body weight. No notable differences among white, black, and Hispanic subjects were seen. The micafungin AUC was greater by 19% in Japanese subjects compared to blacks, due to smaller body weight.

9 DRUG ABUSE AND DEPENDENCE

There has been no evidence of either psychological or physical dependence or withdrawal or rebound effects with micafungin for injection.

10 OVERDOSAGE

Micafungin is highly protein bound and, therefore, is not dialyzable. No cases of micafungin for injection overdosage have been reported. Repeated daily doses up to 8 mg/kg (maximum total dose of 896 mg) in adult patients, up to 6 mg/kg in pediatric patients 4 months of age and older, and up to 15 mg/kg in pediatric patients younger than 4 months of age have been administered in clinical trials with no reported dose-limiting toxicity [see Adverse Reactions (6.1) and Use in Specific Populations (8.4)].

11 DESCRIPTION

Micafungin in Sodium Chloride Injection is a premixed, iso-osmotic, sterile, nonpyrogenic solution for intravenous (IV) infusion that contains micafungin sodium. Micafungin sodium is a semisynthetic lipopeptide (echinocandin).

Micafungin in Sodium Chloride Injection is supplied as a refrigerated 50 mL, 100 mL, or 150 mL single-dose GALAXY container in the following presentations:

50 mg/50 mL (1 mg/mL): containing 50 mg of micafungin (equivalent to 50.87 mg of micafungin sodium); 36 mg citric acid, anhydrous; 450 mg sodium chloride; 92 mg sodium citrate dihydrate;

100 mg/100 mL (1 mg/mL): containing 100 mg of micafungin (equivalent to 101.73 mg of micafungin sodium); 72 mg citric acid, anhydrous; 900 mg sodium chloride; 184 mg sodium citrate dihydrate;

150 mg/150 mL (1 mg/mL): containing 150 mg of micafungin (equivalent to 152.60 mg of micafungin sodium); 108 mg citric acid, anhydrous; 1350 mg sodium chloride; 276 mg sodium citrate dihydrate.

- Each 50 mg/50 mL Galaxy container of Micafungin in Sodium Chloride Injection contains 200 mg of sodium.
- Each 100 mg/100 mL Galaxy container of Micafungin in Sodium Chloride Injection contains 400 mg of sodium.
- Each 150 mg/150 mL Galaxy container of Micafungin in Sodium Chloride Injection contains 600 mg of sodium.

The premixed solution is clear and colorless, with a pH range of 4.5 to 5.1.

Micafungin sodium is chemically designated as:

Pneumocandin A0,1-[(4R,5R)-4,5-dihydroxy-N^2-[4-[5-[4-(pentyloxy) phenyl]-3-isoxazolyl]benzoyl]-L-ornithine]-4-[(4S)-4-hydroxy-4-[4-hydroxy-3-(sulfooxy)phenyl]-L-threonine]-, monosodium salt.

The chemical structure of micafungin sodium is:

The empirical/molecular formula is C56H70N9NaO23S and the formula weight is 1292.26.

Micafungin sodium is a light-sensitive, hygroscopic white powder that is freely soluble in water, isotonic sodium chloride solution, N,N-dimethylformamide and dimethylsulfoxide, slightly soluble in methyl alcohol, and practically insoluble in acetonitrile, ethyl alcohol (95%), acetone, diethyl ether and n-hexane.

12 CLINICAL PHARMACOLOGY

12.1 Mechanism of Action

Micafungin is a member of the echinocandin class of antifungal agents [see Microbiology (12.4)].

12.2 Pharmacodynamics

The pharmacodynamics of micafungin related to hematogenous Candida meningoencephalitis are described in other sections of the prescribing information [see Use in Specific Populations (8.4) and Microbiology (12.4)].

12.3 Pharmacokinetics

The pharmacokinetics of micafungin were determined in healthy subjects, hematopoietic stem cell transplant recipients, and patients with esophageal candidiasis up to a maximum daily dose of 8 mg/kg body weight.

The relationship of area under the concentration-time curve (AUC) to micafungin dose was linear over the daily dose range of 50 mg to 150 mg and 3 mg/kg to 8 mg/kg body weight. Typically, 85% of the steady-state concentration is achieved after three daily micafungin for injection doses.

Steady-state pharmacokinetic parameters in relevant patient populations after repeated daily administration are presented in Table 7.

Table 7. Pharmacokinetic Parameters of Micafungin in Adult Patients
Population | n | Dose (mg) | Pharmacokinetic Parameters (Mean ± Standard Deviation)
Population | n | Dose (mg) | Cmax (mcg/mL) | AUC0-24 [AUC0-infinity is presented for Day 1; AUC0-24 is presented for steady-state.] (mcg h/mL) | t1/2 (h) | Cl (mL/min/kg)
Patients with IC [candidemia or other Candida infections.] [Day 1] | 20 | 100 | 5.7 ± 2.2 | 83 ± 51 | 14.5 ± 7.0 | 0.359 ± 0.179
[Steady-State] | 20 | 100 | 10.1 ± 4.4 | 97 ± 29 | 13.4 ± 2.0 | 0.298 ± 0.115
HIV [human immunodeficiency virus.] – Positive Patients with EC [esophageal candidiasis.] [Day 1] | 20 20 14 | 50 100 150 | 4.1 ± 1.4 8.0 ± 2.4 11.6 ± 3.1 | 36 ± 9 108 ± 31 151 ± 45 | 14.9 ± 4.3 13.8 ± 3.0 14.1 ± 2.6 | 0.321 ± 0.098 0.327 ± 0.093 0.340 ± 0.092
[Day 14 or 21] | 20 20 14 | 50 100 150 | 5.1 ± 1.0 10.1 ± 2.6 16.4 ± 6.5 | 54 ± 13 115 ± 25 167 ± 40 | 15.6 ± 2.8 16.9 ± 4.4 15.2 ± 2.2 | 0.300 ± 0.063 0.301 ± 0.086 0.297 ± 0.081
HSCT [hematopoietic stem cell transplant.] Recipients [Day 7] | 8 10 8 8 | per kg 3 4 6 8 | 21.1 ± 2.84 29.2 ± 6.2 38.4 ± 6.9 60.8 ± 26.9 | 234 ± 34 339 ± 72 479 ± 157 663 ± 212 | 14.0 ± 1.4 14.2 ± 3.2 14.9 ± 2.6 17.2 ± 2.3 | 0.214 ± 0.031 0.204 ± 0.036 0.224 ± 0.064 0.223 ± 0.081

Distribution

The mean ± standard deviation volume of distribution of micafungin at terminal phase was 0.39 ± 0.11 L/kg body weight when determined in adult patients with esophageal candidiasis at the dose range of 50 mg to 150 mg.

Micafungin is highly (greater than 99%) protein bound in vitro, independent of plasma concentrations over the range of 10 to 100 mcg/mL. The primary binding protein is albumin; however, micafungin, at therapeutically relevant concentrations, does not competitively displace bilirubin binding to albumin. Micafungin also binds to a lesser extent to α1-acid-glycoprotein.

Micafungin is neither a substrate nor an inhibitor of P-glycoprotein.

Elimination

Metabolism

Micafungin is metabolized to M-1 (catechol form) by arylsulfatase, with further metabolism to M-2 (methoxy form) by catechol-O-methyltransferase. M-5 is formed by hydroxylation at the side chain (ω-1 position) of micafungin catalyzed by cytochrome P450 (CYP) isozymes. Even though micafungin is a substrate for and a weak inhibitor of CYP3A in vitro, hydroxylation by CYP3A is not a major pathway for micafungin metabolism in vivo. Micafungin is neither a P-glycoprotein substrate nor inhibitor in vitro.

In four healthy volunteer studies, the ratio of metabolite to parent exposure (AUC) at a dose of 150 mg/day was 6% for M-1, 1% for M-2, and 6% for M-5. In patients with esophageal candidiasis, the ratio of metabolite to parent exposure (AUC) at a dose of 150 mg/day was 11% for M-1, 2% for M-2, and 12% for M-5.

Excretion

The excretion of radioactivity following a single intravenous dose of ^14C-micafungin sodium for injection (25 mg) was evaluated in healthy volunteers. At 28 days after administration, mean urinary and fecal recovery of total radioactivity accounted for 82.5% (76.4% to 87.9%) of the administered dose. Fecal excretion is the major route of elimination (total radioactivity at 28 days was 71% of the administered dose).

Specific Populations

Pediatric Patients

Pediatric Patients 4 Months of Age and Older

Micafungin pharmacokinetics in 229 pediatric patients 4 months through 16 years of age were characterized using population pharmacokinetics. Micafungin exposure was dose proportional across the dose and age range studied.

Table 8. Summary (Mean +/- Standard Deviation) of Micafungin Pharmacokinetics in Pediatric Patients 4 Months of Age and Older (Steady-State)
Body weight group | N | Dose [Or the equivalent if receiving the adult dose (50, 100, or 150 mg).] mg/kg | Cmax.ss [Derived from simulations from the population PK model.] (mcg/mL) | AUC.ss (mcg h/mL) | t1/2 [Derived from the population PK model.] (h) | CL mL/min/kg)
30 kg or less | 149 | 1.0 | 7.1 +/- 4.7 | 55 +/- 16 | 12.5 +/- 4.6 | 0.328 +/- 0.091
30 kg or less | 149 | 2.0 | 14.2 +/- 9.3 | 109 +/- 31 | 12.5 +/- 4.6 | 0.328 +/- 0.091
30 kg or less | 149 | 3.0 | 21.3 +/- 14.0 | 164 +/- 47 | 12.5 +/- 4.6 | 0.328 +/- 0.091
Greater than 30 kg | 80 | 1.0 | 8.7 +/- 5.6 | 67 +/- 17 | 13.6 +/- 8.8 | 0.241 +/- 0.061
Greater than 30 kg | 80 | 2.0 | 17.5 +/- 11.2 | 134 +/- 33 | 13.6 +/- 8.8 | 0.241 +/- 0.061
Greater than 30 kg | 80 | 2.5 | 23.0 +/- 14.5 | 176 +/- 42 | 13.6 +/- 8.8 | 0.241 +/- 0.061

Pediatric Patients Younger than 4 Months of Age

Micafungin pharmacokinetic data in 103 pediatric patients less than 4 months of age were assessed using population pharmacokinetics. Predicted micafungin AUC estimates were dose proportional across the dose regimens and age ranges studied. The body weight-normalized micafungin clearance in pediatric patients less than 4 months of age is higher than the body weight-normalized micafungin clearance in older pediatric patients greater than 4 months of age and adults. Administration of 4 mg/kg once daily micafungin to pediatric patients less than 4 months of age produces a mean (SD) steady-state AUC of 131 (50) mcg·h/mL, which is comparable to the steady-state AUC in pediatric patients 4 months of age and older administered micafungin 2 mg/kg/day and adults administered 100 mg once daily.

Patients with Renal Impairment

Micafungin in Sodium Chloride Injection does not require dose adjustment in patients with renal impairment. A single 1-hour infusion of 100 mg micafungin for injection was administered to 9 adult subjects with severe renal impairment (creatinine clearance less than 30 mL/min) and to 9 age-, gender-, and weight-matched subjects with normal renal function (creatinine clearance greater than 80 mL/min). The maximum concentration (Cmax) and AUC were not significantly altered by severe renal impairment.

Since micafungin is highly protein bound, it is not dialyzable. Supplementary dosing should not be required following hemodialysis.

Patients with Hepatic Impairment

- A single 1-hour infusion of 100 mg micafungin for injection was administered to 8 adult subjects with moderate hepatic impairment (Child-Pugh score 7 to 9) and 8 age-, gender-, and weight-matched subjects with normal hepatic function. The Cmax and AUC values of micafungin were lower by approximately 22% in subjects with moderate hepatic impairment compared to normal subjects. This difference in micafungin exposure does not require dose adjustment of Micafungin in Sodium Chloride Injection in patients with moderate hepatic impairment.
- A single 1-hour infusion of 100 mg micafungin for injection was administered to 8 adult subjects with severe hepatic impairment (Child-Pugh score 10 to 12) and 8 age-, gender-, ethnic- and weight-matched subjects with normal hepatic function. The mean Cmax and AUC values of micafungin were lower by approximately 30% in subjects with severe hepatic impairment compared to normal subjects. The mean Cmax and AUC values of M-5 metabolite were approximately 2.3-fold higher in subjects with severe hepatic impairment compared to normal subjects; however, this exposure (parent and metabolite) was comparable to that in patients with systemic Candida infection. Therefore, no Micafungin in Sodium Chloride Injection dose adjustment is necessary in patients with severe hepatic impairment.

12.4 Microbiology

Mechanism of Action

Micafungin inhibits the synthesis of 1,3-beta-D-glucan, an essential component of fungal cell walls, which is not present in mammalian cells.

Activity in Animal Models of Candidiasis

Activity of micafungin has been demonstrated in both mucosal and disseminated murine and rabbit models of candidiasis. Micafungin administered to immunocompetent or immunosuppressed mice or rabbits with disseminated candidiasis prolonged survival (mice) and/or decreased the fungal burden in different organs including brain in a dose-dependent manner (mice and rabbits). Overall, antifungal activity of micafungin was demonstrated in the brain and eye tissues of nonneutropenic rabbits with HCME infected with a micafungin-sensitive strain of C. albicans; however, the activity varied in different central nervous system and ocular compartments. In the cerebrum, culture negativity was achieved at a micafungin dose regimen of 32 mg/kg once daily for 7 days; whereas, in spinal cord, vitreous humor, and choroid, culture negativity was achieved at micafungin dose regimens of 24 to 32 mg/kg once daily. Compared to untreated animals, micafungin dose regimens between 8 and 24 mg/kg once daily reduced fungal burden in the cerebrum and cerebellum. When cerebrum, cerebellum and spinal cord data were combined, a decrease in fungal burden relative to untreated controls was evident at micafungin dose regimens between 16 and 32 mg/kg once daily [see Use in Specific Populations (8.4)].

Resistance

There have been reports of clinical failures in patients receiving micafungin for injection therapy due to the development of drug resistance. Some of these reports have identified specific mutations in the FKS protein component of the glucan synthase enzyme that are associated with higher MICs and breakthrough infection.

Antimicrobial Activity

Micafungin has been shown to be active against most isolates of the following Candida species, both in vitro and in clinical infections [see Indications and Usage (1)]:

Candida albicans

Candida glabrata

Candida guilliermondii

Candida krusei

Candida parapsilosis

Candida tropicalis

Susceptibility Testing

For specific information regarding susceptibility test interpretive criteria and associated test methods and quality control standards recognized by FDA for this drug, please see: https://www.fda.gov/STIC.

13 NONCLINICAL TOXICOLOGY

13.1 Carcinogenesis, Mutagenesis, Impairment of Fertility

Hepatic carcinomas and adenomas were observed in a 6-month intravenous toxicology study with an 18-month recovery period of micafungin sodium in rats designed to assess the reversibility of hepatocellular lesions.

Rats administered micafungin sodium for 3 months at 32 mg/kg/day (corresponding to 8 times the highest recommended human dose [150 mg/day], based on AUC comparisons), exhibited colored patches/zones, multinucleated hepatocytes and altered hepatocellular foci after 1 or 3-month recovery periods, and adenomas were observed after a 21-month recovery period. Rats administered micafungin sodium at the same dose for 6 months exhibited adenomas after a 12-month recovery period; after an 18-month recovery period, an increased incidence of adenomas was observed and, additionally, carcinomas were detected. A lower dose of micafungin sodium (equivalent to 5 times the human AUC) in the 6-month rat study resulted in a lower incidence of adenomas and carcinomas following 18 months recovery. The duration of micafungin dosing in these rat studies (3 or 6 months) exceeds the usual duration of Micafungin in Sodium Chloride Injection dosing in patients, which is typically less than 1 month for treatment of esophageal candidiasis, but dosing may exceed 1 month for Candida prophylaxis.

Although the increase in carcinomas in the 6-month rat study did not reach statistical significance, the persistence of altered hepatocellular foci subsequent to micafungin for injection dosing, and the presence of adenomas and carcinomas in the recovery periods suggest a causal relationship between micafungin sodium, altered hepatocellular foci, and hepatic neoplasms. Whole-life carcinogenicity studies of micafungin for injection in animals have not been conducted, and it is not known whether the hepatic neoplasms observed in treated rats also occur in other species, or if there is a dose threshold for this effect.

Micafungin sodium was not mutagenic or clastogenic when evaluated in a standard battery of in vitro and in vivo tests (i.e., bacterial reversion - S. typhimurium, E. coli; chromosomal aberration; intravenous mouse micronucleus).

Male rats treated intravenously with micafungin sodium for 9 weeks showed vacuolation of the epididymal ductal epithelial cells at or above 10 mg/kg (about 0.6 times the recommended clinical dose for esophageal candidiasis, based on body surface area comparisons). Higher doses (about twice the recommended clinical dose, based on body surface area comparisons) resulted in higher epididymis weights and reduced numbers of sperm cells. In a 39-week intravenous study in dogs, seminiferous tubular atrophy and decreased sperm in the epididymis were observed at 10 and 32 mg/kg, doses equal to about 2 and 7 times the recommended clinical dose, based on body surface area comparisons. There was no impairment of fertility in animal studies with micafungin sodium.

13.2 Animal Toxicology and/or Pharmacology

High doses of micafungin sodium (5 to 8 times the highest recommended human dose, based on AUC comparisons) have been associated with irreversible changes to the liver when administered for 3 or 6 months, and these changes may be indicative of pre-malignant processes [see Nonclinical Toxicology (13.1)].

14 CLINICAL STUDIES

14.1 Treatment of Candidemia and Other Candida Infections in Adult and Pediatric Patients 4 Months of Age and Older

Two dose levels of micafungin for injection were evaluated in a randomized, double-blind study to determine the efficacy and safety versus caspofungin in patients with invasive candidiasis and candidemia. Patients were randomized to receive once daily intravenous infusions (IV) of micafungin for injection, either 100 mg/day or 150 mg/day or caspofungin (70 mg loading dose followed by 50 mg maintenance dose). Patients in both study arms were permitted to switch to oral fluconazole after at least 10 days of intravenous therapy, provided they were non-neutropenic, had improvement or resolution of clinical signs and symptoms, had a Candida isolate which was susceptible to fluconazole, and had documentation of 2 negative cultures drawn at least 24 hours apart. Patients were stratified by APACHE II score (20 or less or greater than 20) and by geographic region. Patients with Candida endocarditis were excluded from this analysis. Outcome was assessed by overall treatment success based on clinical (complete resolution or improvement in attributable signs and symptoms and radiographic abnormalities of the Candida infection and no additional antifungal therapy) and mycological (eradication or presumed eradication) response at the end of IV therapy. Deaths that occurred during IV study drug therapy were treated as failures.

In this study, 111/578 (19.2%) of the patients had baseline APACHE II scores of greater than 20, and 50/578 (8.7%) were neutropenic at baseline (absolute neutrophil count less than 500 cells/mm^3). Outcome, relapse and mortality data are shown for the recommended dose of micafungin for injection (100 mg/day) and caspofungin in Table 9.

Table 9. Efficacy Analysis: Treatment Success in Patients in Study 03-0-192 with Candidemia and Other Candida Infections
 | Micafungin for Injection 100 mg/day n (%) % treatment difference (95% CI) | Caspofungin [70 mg loading dose on day 1 followed by 50 mg/day thereafter (caspofungin).] 70/50 mg/day n (%)
Treatment Success at End of IV Therapy | 135/191 (70.7) 7.4 (-2.0, 16.3) | 119/188 (63.3)
Success in Patients with Neutropenia at Baseline | 14/22 (63.6) | 5/11 (45.5)
Success by Site of Infection
Candidemia | 116/163 (71.2) | 103/161 (64)
Abscess | 4/5 (80) | 5/9 (55.6)
Acute Disseminated [A patient may have had greater than 1 organ of dissemination.] | 6/13 (46.2) | 5/9 (55.6)
Endophthalmitis | 1/3 | 1/1
Chorioretinitis | 0/3 | 0
Skin | 1/1 | 0
Kidney | 2/2 | 1/1
Pancreas | 1/1 | 0
Peritoneum | 1/1 | 0
Lung/Skin | 0/1 | 0
Lung/Spleen | 0/1 | 0
Liver | 0 | 0/2
Intraabdominal abscess | 0 | 3/5
Chronic Disseminated | 0/1 | 0
Peritonitis | 4/6 (66.7) | 2/5 (40)
Success by Organism [A patient may have had greater than 1 baseline infection species.]
C. albicans | 57/81 (70.4) | 45/73 (61.6)
C. glabrata | 16/23 (69.6) | 19/31 (61.3)
C. tropicalis | 17/27 (63) | 22/29 (75.9)
C. parapsilosis | 21/28 (75) | 22/39 (56.4)
C. krusei | 5/8 (62.5) | 2/3 (66.7)
C. guilliermondii | 1/2 | 0/1
C. lusitaniae | 2/3 (66.7) | 2/2
Relapse through 6 Weeks [All patients who had a culture-confirmed relapse or required systemic antifungal therapy in the post-treatment period for a suspected or proven Candida infection. Also includes patients who died or were not assessed in follow-up.]
Overall | 49/135 (36.3) | 44/119 (37)
Culture-confirmed relapse | 5 | 4
Required systemic antifungal therapy | 11 | 5
Died during follow-up | 17 | 16
Not assessed | 16 | 19
Overall study mortality | 58/200 (29) | 51/193 (26.4)
Mortality during IV therapy | 28/200 (14) | 27/193 (14)

In two cases of ophthalmic involvement assessed as failures in the above table due to missing evaluation at the end of IV treatment with micafungin for injection, therapeutic success was documented during protocol-defined oral fluconazole therapy.

14.2 Treatment of Esophageal Candidiasis in Adult and Pediatric Patients 4 Months of Age and Older

In two controlled trials involving 763 patients with esophageal candidiasis, 445 adults with endoscopically-proven candidiasis received micafungin for injection, and 318 received fluconazole for a median duration of 14 days (range 1 to 33 days).

Micafungin for injection was evaluated in a randomized, double-blind study which compared micafungin for injection 150 mg/day (n = 260) to intravenous fluconazole 200 mg/day (n = 258) in adults with endoscopically-proven esophageal candidiasis. Most patients in this study had HIV infection, with CD4 cell counts less than 100 cells/mm^3. Outcome was assessed by endoscopy and by clinical response at the end of treatment. Endoscopic cure was defined as endoscopic grade 0, based on a scale of 0 to 3. Clinical cure was defined as complete resolution in clinical symptoms of esophageal candidiasis (dysphagia, odynophagia, and retrosternal pain). Overall therapeutic cure was defined as both clinical and endoscopic cure. Mycological eradication was determined by culture, and by histological or cytological evaluation of esophageal biopsy or brushings obtained endoscopically at the end of treatment. As shown in Table 10, endoscopic cure, clinical cure, overall therapeutic cure, and mycological eradication were comparable for patients in the micafungin for injection and fluconazole treatment groups.

Table 10. Endoscopic, Clinical, and Mycological Outcomes for Esophageal Candidiasis at End-of-Treatment
Treatment Outcome [Endoscopic and clinical outcome were measured in the modified intent-to-treat population, including all randomized patients who received 1 or more doses of study treatment. The mycological outcome was determined in the per protocol (evaluable) population, including patients with confirmed esophageal candidiasis who received at least 10 doses of study drug, and had no major protocol violations.] | Micafungin for Injection 150 mg/day n = 260 | Fluconazole 200 mg/day n = 258 | % Difference [Calculated as micafungin for injection – fluconazole.] (95% CI)
Endoscopic Cure | 228 (87.7%) | 227 (88.0%) | -0.3% (-5.9, +5.3)
Clinical Cure | 239 (91.9%) | 237 (91.9%) | 0.06% (-4.6, +4.8)
Overall Therapeutic Cure | 223 (85.8%) | 220 (85.3%) | 0.5% (-5.6, +6.6)
Mycological Eradication | 141/189 (74.6%) | 149/192 (77.6%) | -3.0% (-11.6, +5.6)

Most patients (96%) in this study had C. albicans isolated at baseline. The efficacy of micafungin for injection was evaluated in less than 10 patients with Candida species other than C. albicans, most of which were isolated concurrently with C. albicans. Relapse was assessed at 2 and 4 weeks post-treatment in patients with overall therapeutic cure at end of treatment. Relapse was defined as a recurrence of clinical symptoms or endoscopic lesions (endoscopic grade greater than 0). There was no statistically significant difference in relapse rates at either 2 weeks or through 4 weeks post-treatment for patients in the micafungin for injection and fluconazole treatment groups, as shown in Table 11.

Table 11. Relapse of Esophageal Candidiasis at Week 2 and through Week 4 Post-Treatment in Patients with Overall Therapeutic Cure at the End of Treatment
Relapse | Micafungin for Injection 150 mg/day n = 223 | Fluconazole 200 mg/day n = 220 | % Difference [Calculated as micafungin for injection – fluconazole; N = number of patients with overall therapeutic cure (both clinical and endoscopic cure at end-of-treatment);] (95% CI)
Relapse [Relapse included patients who died or were lost to follow-up, and those who received systemic anti-fungal therapy in the post-treatment period.] at Week 2 | 40 (17.9%) | 30 (13.6%) | 4.3% (-2.5, 11.1)
Relapse through Week 4 (cumulative) | 73 (32.7%) | 62 (28.2%) | 4.6% (-4.0, 13.1)

In this study, 459 of 518 (88.6%) patients had oropharyngeal candidiasis in addition to esophageal candidiasis at baseline. At the end of treatment, 192/230 (83.5%) micafungin for injection-treated patients and 188/229 (82.1%) of fluconazole-treated patients experienced resolution of signs and symptoms of oropharyngeal candidiasis. Of these, 32.3% in the micafungin for injection group, and 18.1% in the fluconazole group (treatment difference = 14.2%; 95% confidence interval [5.6, 22.8]) had symptomatic relapse at 2 weeks post-treatment. Relapse included patients who died or were lost to follow-up, and those who received systemic antifungal therapy during the post-treatment period. Cumulative relapse at 4 weeks post-treatment was 52.1% in the micafungin for injection group and 39.4% in the fluconazole group (treatment difference 12.7%, 95% confidence interval [2.8, 22.7]).

14.3 Prophylaxis of Candida Infections in Hematopoietic Stem Cell Transplant Recipients

In a randomized, double-blind study, micafungin for injection (50 mg IV once daily) was compared to fluconazole (400 mg IV once daily) in 882 [adult (791) and pediatric (91)] patients undergoing an autologous or syngeneic (46%) or allogeneic (54%) stem cell transplant. All pediatric patients, except 2 per group, received allogeneic transplants. The status of the patients’ underlying malignancy at the time of randomization was: 365 (41%) patients with active disease, 326 (37%) patients in remission, and 195 (22%) patients in relapse. The more common baseline underlying diseases in the 476 allogeneic transplant recipients were: chronic myelogenous leukemia (22%), acute myelogenous leukemia (21%), acute lymphocytic leukemia (13%), and non-Hodgkin’s lymphoma (13%). In the 404 autologous and syngeneic transplant recipients the more common baseline underlying diseases were: multiple myeloma (37.1%), non-Hodgkin’s lymphoma (36.4%), and Hodgkin's disease (15.6%). During the study, 198 of 882 (22.4%) transplant recipients had proven graft-versus-host disease; and 475 of 882 (53.9%) recipients received immunosuppressive medications for treatment or prophylaxis of graft-versus-host disease.

Study drug was continued until the patient had neutrophil recovery to an absolute neutrophil count (ANC) of 500 cells/mm^3 or greater or up to a maximum of 42 days after transplant. The average duration of drug administration was 18 days (range 1 to 51 days). Duration of therapy was slightly longer in the pediatric patients who received micafungin for injection (median duration 22 days) compared to the adult patients who received micafungin for injection (median duration 18 days).

Successful prophylaxis was defined as the absence of a proven, probable, or suspected systemic fungal infection through the end of therapy (usually 18 days), and the absence of a proven or probable systemic fungal infection through the end of the 4-week post-therapy period. A suspected systemic fungal infection was diagnosed in patients with neutropenia (ANC less than 500 cells/mm^3); persistent or recurrent fever (while ANC less than 500 cells/mm^3) of no known etiology; and failure to respond to at least 96 hours of broad spectrum antibacterial therapy. A persistent fever was defined as four consecutive days of fever greater than 38ºC. A recurrent fever was defined as having at least one day with temperatures 38.5ºC or higher after having at least one prior temperature higher than 38ºC; or having two days of temperatures higher than 38ºC after having at least one prior temperature higher than 38ºC. Transplant recipients who died or were lost to follow-up during the study were considered failures of prophylactic therapy.

Successful prophylaxis was documented in 80.7% of adult and pediatric micafungin for injection recipients, and in 73.7% of adult and pediatric patients who received fluconazole (7.0% difference [95% CI = 1.5, 12.5]), as shown in Table 12, along with other study endpoints. The use of systemic antifungal therapy post-treatment was 42% in both groups.

The number of proven breakthrough Candida infections was 4 in the micafungin for injection and 2 in the fluconazole group.

The efficacy of micafungin for injection against infections caused by fungi other than Candida has not been established.

Table 12. Results from Clinical Study of Prophylaxis of Candida Infections in Hematopoietic Stem Cell Transplant Recipients
Outcome of Prophylaxis | Micafungin for Injection 50 mg/day (n = 425) | Fluconazole 400 mg/day (n = 457)
Success [Difference (micafungin for injection – fluconazole): +7.0% [95% CI=1.5, 12.5].] | 343 (80.7%) | 337 (73.7%)
Failure: | 82 (19.3%) | 120 (26.3%)
All Deaths [Through end-of-study (4 weeks post-therapy).] | 18 (4.2%) | 26 (5.7%)
Proven/probable fungal infection prior to death | 1 (0.2%) | 3 (0.7%)
Proven/probable fungal infection (not resulting in death) | 6 (1.4%) | 8 (1.8%)
Suspected fungal infection [Through end-of-therapy.] | 53 (12.5%) | 83 (18.2%)
Lost to follow-up | 5 (1.2%) | 3 (0.7%)

16 HOW SUPPLIED/STORAGE AND HANDLING

How Supplied

Micafungin in Sodium Chloride Injection is supplied as a clear and colorless refrigerated, premixed, iso-osmotic, sterile, nonpyrogenic solution for intravenous infusion, and is available in the following packaging configurations:

Code | NDC Multiple Cartons | NDC Individual Carton | Size | Number of Containers/Carton
2G3434 | NDC 0338-9051-12 | NDC 0338-9051-01 | 50 mL | 12 individually packaged 50 mg/50 mL (1 mg/mL) single-dose Galaxy containers
2G3435 | NDC 0338-9053-12 | NDC 0338-9053-01 | 100 mL | 12 individually packaged 100 mg/100 mL (1 mg/mL) single-dose Galaxy containers
2G3433 | NDC 0338-9055-10 | NDC 0338-9055-01 | 150 mL | 10 individually packaged 150 mg/150 mL (1 mg/mL) single-dose Galaxy containers

Storage and Handling

Store Micafungin in Sodium Chloride Injection in the refrigerator at 2°C to 8°C (36°F to 46°F) in the original carton to protect from light. Do not use after the expiration date printed on the carton and container label.

If needed, Micafungin in Sodium Chloride Injection may be stored at room temperature 20°C to 25°C (68°F to 77°F) for up to 30 days in the original carton to protect from light. Once stored at room temperature, do not place back in the refrigerator. Discard Micafungin in Sodium Chloride Injection after 30 days if stored at room temperature.

Do not freeze and do not use Micafungin in Sodium Chloride Injection if it has been frozen.

17 PATIENT COUNSELING INFORMATION

Hypersensitivity

Inform patients about the serious adverse effects of Micafungin in Sodium Chloride Injection including hypersensitivity reactions, e.g., anaphylaxis and anaphylactoid reactions including shock.

Hepatic

Inform patients about the serious adverse effects of Micafungin in Sodium Chloride Injection including hepatic effects, e.g., abnormal liver tests, hepatic impairment, hepatitis or worsening hepatic failure.

Hematologic

Inform patients about the serious adverse effects of Micafungin in Sodium Chloride Injection including hematological effects, e.g., acute intravascular hemolysis, hemolytic anemia and hemoglobinuria.

Renal

Inform patients about the serious adverse effects of Micafungin in Sodium Chloride Injection including renal effects, e.g., elevations in BUN and creatinine, renal impairment or acute renal failure.

Embryo-Fetal Toxicity

Advise pregnant women and females of reproductive potential of the potential risk of Micafungin in Sodium Chloride Injection to a fetus. Advise females to inform their healthcare provider of a known or suspected pregnancy.

Concomitant Medications

Instruct patients to inform their healthcare provider of any other medications they are currently taking with Micafungin in Sodium Chloride Injection, including over-the-counter medications.

High Sodium Load

Advise patients to inform their healthcare provider if they are on a salt-restricted diet or have congestive heart failure as increased blood sodium can occur in people who receive Micafungin in Sodium Chloride Injection [see Warnings and Precautions (5.6)].

Baxter Logo

Manufactured by:

Baxter Healthcare Corporation

Deerfield, IL 60015 USA

Product of USA

Baxter and Galaxy are registered trademarks of Baxter International Inc.

07-19-06-083

PACKAGE/LABEL PRINCIPAL DISPLAY PANEL

Container Label

NDC 0338-9051-01

Micafungin
in 0.9% Sodium Chloride Injection
50 mg / 50 mL (1 mg / mL)

50 mg
TOTAL

50 mL Single-Dose GALAXY container
Discard unused portion
For Intravenous Infusion Only

Rx only
Sterile Nonpyrogenic

Cautions: Do not add supplemental medication or additives.
Must not be used in series connections. Check for minute leaks and solution
clarity.

Each 50 mL bag contains: 50 mg of Micafungin Sodium (equivalent to 50.87 mg of
Micafungin Sodium); 36 mg Citric Acid, Anhydrous; 450 mg Sodium Chloride,
92 mg Sodium Citrate, Dihydrate; and Water for Injection.

Dosage: See prescribing information.

Store refrigerated at 2°C to 8°C (36°F to 46°F) in the original carton to
protect from light. Do Not Freeze.

If needed, may store at room temperature up to 25°C (77°F) up to 30 days in
the original carton. Discard after 30 days if stored at room temperature.

Baxter Logo

Baxter and Galaxy are registered trademarks of Baxter International Inc.
Baxter Healthcare Corporation, Deerfield, IL 60015 USA

Code 2G3434
PL 2501 Plastic

Product of USA
07-34-00-1662

BAR CODE
POSITION ONLY UPCA-A

XXXXXXXXXXXX

Container Label

NDC 0338-9053-01

Micafungin
in 0.9% Sodium Chloride Injection
100 mg / 100 mL (1 mg / mL)

100 mg
TOTAL

100 mL Single-Dose GALAXY container
Discard unused portion
For Intravenous Infusion Only

Rx only
Sterile Nonpyrogenic

Cautions: Do not add supplemental medication or additives.
Must not be used in series connections. Check for minute leaks
and solution clarity.

Each mL contains: 100 mg of Micafungin (equivalent
to 101.73 mg of Micafungin Sodium); 72 mg Citric Acid,
Anhydrous; 900 mg Sodium Chloride; 184 mg Sodium Citrate,
Dihydrate; and Water for Injection.

Dosage: See prescribing information.

Store refrigerated at 2°C to 8°C (36°F to 46°F) in the original
carton to protect from light. Do Not Freeze.

If needed, may store at room temperature up to 25°C (77°F) up
to 30 days in the original carton. Discard after 30 days if stored at
room temperature.

Baxter Logo

Baxter and Galaxy are registered trademarks of
Baxter International Inc.
Baxter Healthcare Corporation,
Deerfield, IL 60015 USA

Code 2G3435
PL 2501 Plastic

Product of USA
07-34-00-1663

BAR CODE
POSITION ONLY UPCA-A

XXXXXXXXXXXX

Container Label

NDC 0338-9055-01

Micafungin
in 0.9% Sodium Chloride Injection
150 mg / 150 mL (1 mg / mL)

150 mg
TOTAL

150 mL Single-Dose GALAXY container
Discard unused portion
For Intravenous Infusion Only

Rx only
Sterile Nonpyrogenic

Cautions: Do not add supplemental medication or additives.
Must not be used in series connections. Check for minute leaks
and solution clarity.

Each mL contains: 150 mg of Micafungin (equivalent
to 152.60 mg of Micafungin Sodium); 108 mg Citric Acid,
Anhydrous; 1350 mg Sodium Chloride; 276 mg Sodium Citrate,
Dihydrate; and Water for Injection.

Dosage: See prescribing information.

Store refrigerated at 2°C to 8°C (36°F to 46°F) in the original
carton to protect from light. Do Not Freeze.

If needed, may store at room temperature up to 25°F (77°F) up
to 30 days in the original carton. Discard after 30 days if stored at
room temperature.

Baxter Logo

Baxter and Galaxy are registered trademarks of
Baxter International Inc.
Baxter Healthcare Corporation,
Deerfield, IL 60015 USA

Code 2G3433
PL 2501 Plastic

Product of USA
07-34-00-1664

BAR CODE
POSITION ONLY UPCA-A

XXXXXXXXXXXX

Carton Label

For Intravenous Only
Micafungin
in 0.9% Sodium Chloride Injection

50 mg per 50 mL (1 mg / mL)

For Intravenous Only
Micafungin
in 0.9% Sodium Chloride Injection

50 mg per 50 mL (1 mg / mL)

NDC 0338-9051-01

Sterile, Nonpyrogenic

Micafungin
in 0.9% Sodium Chloride Injection
50 mg / 50 mL (1 mg / mL)

50 mg
TOTAL

UNVARNISHED AREA FOR ON-LINE
PRINTING OF LOT & EXP

FPO UPC-A Barcode
085412XXXXXX

Each 50 mL bag contains: 50 mg of Micafungin (equivalent to 50.87 mg of Micafungin Sodium);
36 mg Citric Acid, Anhydrous; 450 mg Sodium Chloride; 92 mg Sodium Citrate, Dihydrate;
and Water for Injection.

Dosage: For Intravenous Infusion Only. See prescribing information.

Caution: Do not add supplemental medication or additives.

RX only

Store refrigerated at 2°C to 8°C (36°F to 46°F) in the original carton to protect from light.
Do Not Freeze

If needed, may store at room temperature up to 25°C (77°F) up to 30 days in the original carton.
Once stored at room temperature, do not place back in the refrigerator.
Discard after 30 days if stored at room temperature

Discard 30 days after storing at room temperature. Discard after:
(Month) (Day) (Year)
(to be completed by dispensing pharmacist)

Baxter and Galaxy are registered trademarks of Baxter International Inc.
Baxter Healthcare Corporation
Deerfield, IL 60015 USA

Product of USA
07-01-00-0593

For Intravenous Infusion Only
Micafungin
in 0.9% Sodium Chloride Injection

50 mg per 50 mL (1 mg / mL)

For Intravenous Infusion Only
Micafungin
in 0.9% Sodium Chloride Injection

50 mg per 50 mL (1 mg / mL)

NDC 0338-9051-01

Code 2G3434

Micafungin
in 0.9% Sodium Chloride Injection
50 mg / 50 mL (1 mg / 1 mL)

50 mg
TOTAL

Rx Only

For Intravenous Infusion Only

1 Single-Dose GALAXY Container
Discard unused portion

USE CARTON TO PROECT CONTENTS
FROM LIGHT UNTIL ADMINISTRATION

Baxter Logo

Carton Label

For Intravenous Only
Micafungin
in 0.9% Sodium Chloride Injection

100 mg per 100 mL (1 mg / mL)

For Intravenous Only
Micafungin
in 0.9% Sodium Chloride Injection

100 mg per 100 mL (1 mg / mL)

NDC 0338-9053-01

Sterile, Nonpyrogenic

Micafungin
in 0.9% Sodium Chloride Injection
100 mg / 100 mL (1 mg / mL)

100 mg
TOTAL

UNVARNISHED AREA FOR ON-LINE
PRINTING OF LOT & EXP

FPO UPC-A Barcode
085412XXXXXX

Each 100 mL bag contains: 100 mg of Micafungin (equivalent to 101.73 mg of Micafungin Sodium);
72 mg Citric Acid, Anhydrous; 900 mg Sodium Chloride; 184 mg Sodium Citrate, Dihydrate;
and Water for Injection.

Dosage: For Intravenous Infusion Only. See prescribing information.

Caution: Do not add supplemental medication or additives.

RX only

Store refrigerated at 2°C to 8°C (36°F to 46°F) in the original carton to protect from light.
Do Not Freeze

If needed, may store at room temperature up to 25°C (77°F) up to 30 days in the original carton.
Once stored at room temperature, do not place back in the refrigerator.
Discard after 30 days if stored at room temperature

Discard 30 days after storing at room temperature. Discard after:
(Month) (Day) (Year)
(to be completed by dispensing pharmacist)

Baxter and Galaxy are registered trademarks of Baxter International Inc.
Baxter Healthcare Corporation
Deerfield, IL 60015 USA

Product of USA
07-01-00-0613

For Intravenous Infusion Only
Micafungin
in 0.9% Sodium Chloride Injection

100 mg per 100 mL (1 mg / mL)

For Intravenous Infusion Only
Micafungin
in 0.9% Sodium Chloride Injection

100 mg per 100 mL (1 mg / mL)

NDC 0338-9053-01

Code 2G3435

Micafungin
in 0.9% Sodium Chloride Injection
100 mg / 100 mL (1 mg / 1 mL)

100 mg
TOTAL

Rx Only

For Intravenous Infusion Only

1 Single-Dose GALAXY Container
Discard unused portion

USE CARTON TO PROECT CONTENTS
FROM LIGHT UNTIL ADMINISTRATION

Baxter Logo

Carton Label

For Intravenous Only
Micafungin
in 0.9% Sodium Chloride Injection

150 mg per 150 mL (1 mg / mL)

For Intravenous Only
Micafungin
in 0.9% Sodium Chloride Injection

150 mg per 150 mL (1 mg / mL)

NDC 0338-9055-01

Sterile, Nonpyrogenic

Micafungin
in 0.9% Sodium Chloride Injection
150 mg / 150 mL (1 mg / mL)

150 mg
TOTAL

UNVARNISHED AREA FOR ON-LINE
PRINTING OF LOT & EXP

FPO UPC-A Barcode
085412XXXXXX

Each 150 mL bag contains: 150 mg of Micafungin (equivalent to 152.60 mg of Micafungin
Sodium); 108 mg Citric Acid, Anhydrous; 1350 mg Sodium Chloride; 276 mg Sodium Citrate,
Dihydrate; and Water for Injection.

Dosage: For Intravenous Infusion Only. See prescribing information.

Caution: Do not add supplemental medication or additives.

RX only

Store refrigerated at 2°C to 8°C (36°F to 46°F) in the original carton to protect from light.
Do Not Freeze

If needed, may store at room temperature up to 25°C (77°F) up to 30 days in the original carton.
Once stored at room temperature, do not place back in the refrigerator.
Discard after 30 days if stored at room temperature

Discard 30 days after storing at room temperature. Discard after:
(Month) (Day) (Year)
(to be completed by dispensing pharmacist)

Baxter and Galaxy are registered trademarks of Baxter International Inc.
Baxter Healthcare Corporation
Deerfield, IL 60015 USA

Product of USA
07-01-00-0614

For Intravenous Infusion Only
Micafungin
in 0.9% Sodium Chloride Injection

150 mg per 150 mL (1 mg / mL)

For Intravenous Infusion Only
Micafungin
in 0.9% Sodium Chloride Injection

150 mg per 150 mL (1 mg / mL)

NDC 0338-9055-01

Code 2G3433

Micafungin
in 0.9% Sodium Chloride Injection
150 mg / 150 mL (1 mg / 1 mL)

150 mg
TOTAL

Rx Only

For Intravenous Infusion Only

1 Single-Dose GALAXY Container
Discard unused portion

USE CARTON TO PROECT CONTENTS
FROM LIGHT UNTIL ADMINISTRATION

Baxter Logo